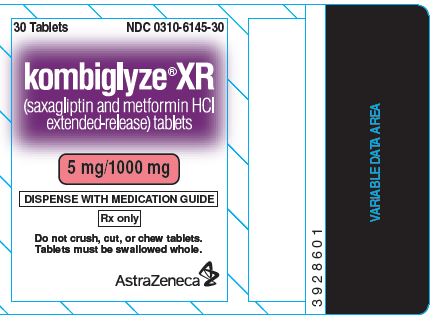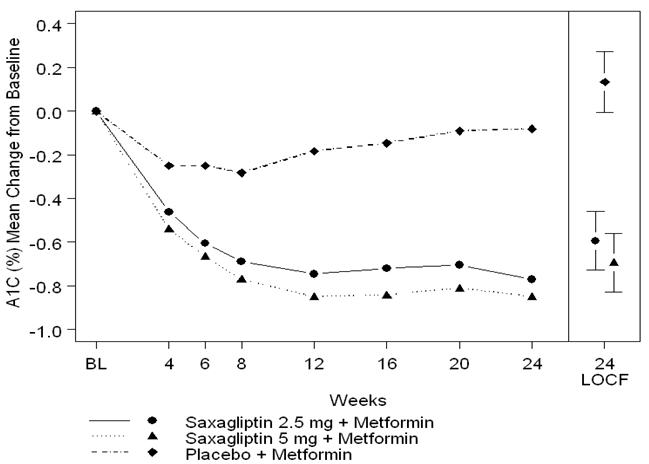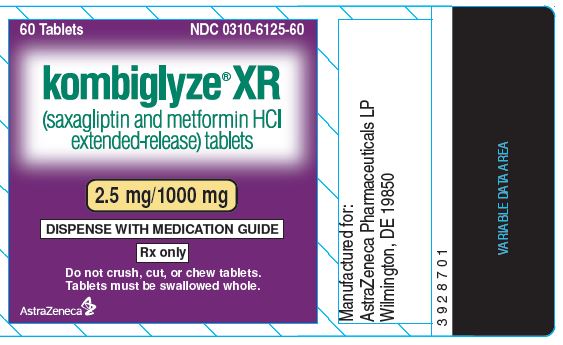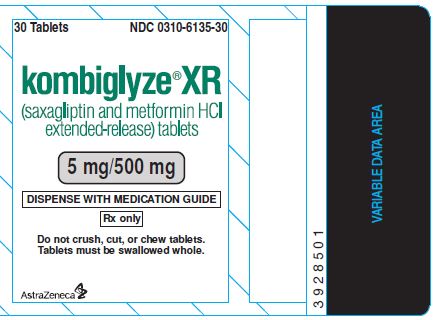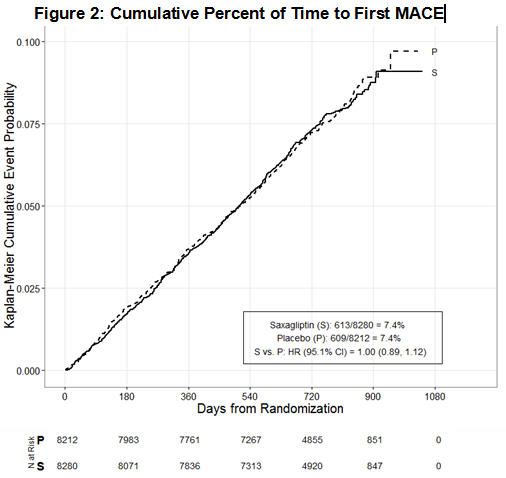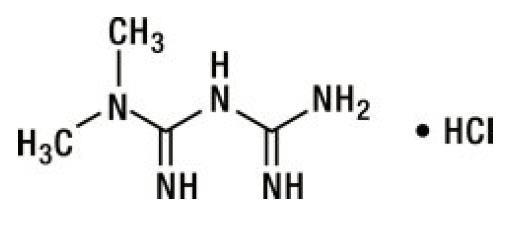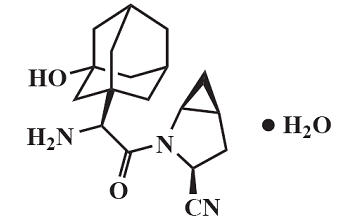 DRUG LABEL: KOMBIGLYZE
NDC: 0310-6125 | Form: TABLET, FILM COATED, EXTENDED RELEASE
Manufacturer: AstraZeneca Pharmaceuticals LP
Category: prescription | Type: HUMAN PRESCRIPTION DRUG LABEL
Date: 20250811

ACTIVE INGREDIENTS: saxagliptin hydrochloride 2.5 mg/1 1; metformin hydrochloride 1000 mg/1 1
INACTIVE INGREDIENTS: hypromellose 2208 (15000 mpa.s); magnesium stearate; CARBOXYMETHYLCELLULOSE SODIUM, UNSPECIFIED

HIGHLIGHTS OF PRESCRIBING INFORMATION

These highlights do not include all the information needed to use KOMBIGLYZE XR safely and effectively. See full prescribing information for KOMBIGLYZE XR.
KOMBIGLYZE® XR (saxagliptin and metformin hydrochloride extended-release) tablets, for oral use
Initial U.S. Approval: 2010

WARNING: LACTIC ACIDOSIS

See full prescribing information for complete boxed warning.

- Post-marketing cases of metformin-associated lactic acidosis have resulted in death, hypothermia, hypotension, and resistant bradyarrhythmias. Symptoms included malaise, myalgias, respiratory distress, somnolence, and abdominal pain. Laboratory abnormalities included elevated blood lactate levels, anion gap acidosis, increased lactate/pyruvate ratio; and metformin plasma levels generally >5 mcg/mL. (5.1)
- Risk factors include renal impairment, concomitant use of certain drugs, age >65 years old, radiological studies with contrast, surgery and other procedures, hypoxic states, excessive alcohol intake, and hepatic impairment. Steps to reduce the risk of and manage metformin-associated lactic acidosis in these high risk groups are provided in the Full Prescribing Information. (5.1)
- If lactic acidosis is suspected, discontinue KOMBIGLYZE XR and institute general supportive measures in a hospital setting. Prompt hemodialysis is recommended. (5.1)

1 INDICATIONS AND USAGE

KOMBIGLYZE XR is a combination of saxagliptin, a dipeptidyl peptidase-4 (DPP4) inhibitor, and metformin hydrochloride (HCl), a biguanide, indicated as an adjunct to diet and exercise to improve glycemic control in adults with type 2 diabetes mellitus. (1)

Limitations of Use:

- Not recommended for the treatment of type 1 diabetes mellitus or diabetic ketoacidosis. (1.1)

2 DOSAGE AND ADMINISTRATION

- Administer once daily with the evening meal. (2.1)
- Individualize the starting dosage based on the patient’s current regimen then adjust the dosage based on effectiveness and tolerability. (2.1)
- Do not exceed a daily dosage of 5 mg saxagliptin/2,000 mg metformin HCl extended-release. (2.1)
- Swallow whole. Never crush, cut, or chew. (2.1)
- Limit the saxagliptin dosage to 2.5 mg daily for patients also taking strong cytochrome P450 3A4/5 inhibitors (e.g., ketoconazole). (2.3, 7.1)
- Assess renal function prior to initiation of KOMBIGLYZE XR and periodically thereafter. (2.2)
  - Do not use in patients with eGFR below 30 mL/min/1.73 m^2.
  - Initiation is not recommended in patients with eGFR between 30 - 45 mL/min/1.73 m^2.
  - Assess risk/benefit of continuing if eGFR falls below 45 mL/min/1.73 m^2.
  - Limit the saxagliptin component to 2.5 mg daily if eGFR is less than 45 mL/min/1.73 m^2.
  - Discontinue if eGFR falls below 30 mL/min/1.73 m^2.
- KOMBIGLYZE XR may need to be discontinued at time of, or prior to, iodinated contrast imaging procedures. (2.4)

3 DOSAGE FORMS AND STRENGTHS

- 5 mg saxagliptin/500 mg metformin HCl extended-release (3)
- 5 mg saxagliptin/1,000 mg metformin HCl extended-release (3)
- 2.5 mg saxagliptin/1,000 mg metformin HCl extended-release (3)

4 CONTRAINDICATIONS

- Severe renal impairment (eGFR below 30 mL/min/1.73 m^2). (4)
- Metabolic acidosis, including diabetic ketoacidosis. (4)
- History of a serious hypersensitivity reaction (e.g., anaphylaxis, angioedema, exfoliative skin conditions) to saxagliptin, metformin HCl, or any of the ingredients in KOMBIGLYZE XR. (4)

5 WARNINGS AND PRECAUTIONS

- Pancreatitis: There have been postmarketing reports of acute pancreatitis. If pancreatitis is suspected, promptly discontinue KOMBIGLYZE XR. (5.2)
- Heart Failure: Consider the risks and benefits of KOMBIGLYZE XR in patients who have known risk factors for heart failure. Monitor patients for signs and symptoms. (5.3)
- Vitamin B12 Deficiency: Metformin may lower vitamin B12 levels. Measure hematological parameters annually. (5.4)
- Hypoglycemia with Concomitant Use of Insulin or Insulin Secretagogues: Consider a lower dosage of insulin or insulin secretagogue when used in combination with KOMBIGLYZE XR. (5.5)
- Hypersensitivity-Related Events: There have been post-marketing reports of serious hypersensitivity reactions, such as anaphylaxis, angioedema, and exfoliative skin conditions in patients treated with saxagliptin. If hypersensitivity reactions occur, discontinue KOMBIGLYZE XR, treat promptly, and monitor until signs and symptoms resolve. (5.6)
- Arthralgia: Severe and disabling arthralgia has been reported in patients taking DPP4 inhibitors. Consider as a possible cause for severe joint pain and discontinue drug if appropriate. (5.7)
- Bullous Pemphigoid: There have been postmarketing reports of bullous pemphigoid requiring hospitalization in patients taking DPP-4 inhibitors. Tell patients to report development of blisters or erosions. If bullous pemphigoid is suspected, discontinue KOMBIGLYZE XR (5.8).

6 ADVERSE REACTIONS

- Most common adverse reactions with metformin HCl extended-release (incidence >5% and more often than placebo) are: diarrhea and nausea/vomiting. (6.1)
- Most common adverse reactions with saxagliptin (incidence ≥5% and more often than placebo) are: upper respiratory tract infection, urinary tract infection, and headache. (6.1)
- Adverse reactions with coadministered saxagliptin and metformin HCl (incidence ≥5% and more often than placebo) are: headache and nasopharyngitis. (6.1)

To report SUSPECTED ADVERSE REACTIONS, contact AstraZeneca at 1-800-236-9933 or FDA at 1-800-FDA-1088 or www.fda.gov/medwatch.

7 DRUG INTERACTIONS

- Strong CYP3A4/5 inhibitors (e.g., ketoconazole): Coadministration with KOMBIGLYZE XR significantly increases saxagliptin concentrations. Limit KOMBIGLYZE XR dosage to 2.5 mg/1,000 mg once daily when coadministered with a strong CYP3A4/5 inhibitor. (2.3, 7.1)
- Carbonic anhydrase inhibitors: May increase risk of lactic acidosis. Consider more frequent monitoring. (7.2)
- Drugs that reduce metformin clearance: May increase risk of lactic acidosis. Consider benefits and risks of concomitant use. (7.3)
- See full prescribing information for additional drug interactions. (7)

8 USE IN SPECIFIC POPULATIONS

- Geriatric Use: Assess renal function more frequently. (8.5)
- Hepatic Impairment: Avoid use in patients with hepatic impairment. (8.7)

FULL PRESCRIBING INFORMATION

WARNING: LACTIC ACIDOSIS

• Post-marketing cases of metformin-associated lactic acidosis have resulted in death, hypothermia, hypotension, and resistant bradyarrhythmias. The onset of metformin-associated lactic acidosis is often subtle, accompanied only by nonspecific symptoms such as malaise, myalgias, respiratory distress, somnolence, and abdominal pain. Metformin-associated lactic acidosis was characterized by elevated blood lactate levels (> 5 mmol/Liter), anion gap acidosis (without evidence of ketonuria or ketonemia), an increased lactate/pyruvate ratio; and metformin plasma levels generally >5 mcg/mL [see Warnings and Precautions (5.1)].

• Risk factors for metformin-associated lactic acidosis include renal impairment, concomitant use of certain drugs (e.g., carbonic anhydrase inhibitors such as topiramate), age 65 years old or greater, having a radiological study with contrast, surgery and other procedures, hypoxic states (e.g., acute congestive heart failure), excessive alcohol intake, and hepatic impairment.

• Steps to reduce the risk of and manage metformin-associated lactic acidosis in these high risk groups are provided in the full prescribing information [see Dosage and Administration (2.2), Contraindications (4), Warnings and Precautions (5.1), Drug Interactions (7), and Use in Specific Populations (8.6, 8.7)].

• If metformin-associated lactic acidosis is suspected, immediately discontinue KOMBIGLYZE XR and institute general supportive measures in a hospital setting. Prompt hemodialysis is recommended [see Warnings and Precautions (5.1)].

1 INDICATIONS AND USAGE

KOMBIGLYZE XR is indicated as an adjunct to diet and exercise to improve glycemic control in adults with type 2 diabetes mellitus [see Clinical Studies (14)].

1.1 Limitations of Use

KOMBIGLYZE XR is not recommended for the treatment of type 1 diabetes mellitus or diabetic ketoacidosis.

2 DOSAGE AND ADMINISTRATION

2.1 Recommended Dosage and Administration

Individualize the starting dosage of KOMBIGLYZE XR based on the patient’s current regimen and the available strengths of KOMBIGLYZE XR [see Dosage Forms and Strengths (3)].

Administer KOMBIGLYZE XR once daily with the evening meal, with gradual dose titration to reduce the gastrointestinal side effects associated with metformin HCl [see Adverse Reactions (6.1)].

The recommended starting dosage of KOMBIGLYZE XR in patients who need 5 mg of saxagliptin and who are not currently treated with metformin HCl is one KOMBIGLYZE XR tablet containing 5 mg saxagliptin and 500 mg metformin HCl extended-release once daily with gradual dose escalation to reduce the gastrointestinal side effects due to metformin HCl.

In patients treated with metformin HCl, the recommended starting dosage of KOMBIGLYZE XR should provide metformin HCl at the dose already being taken, or the nearest therapeutically appropriate dose. Following a switch from metformin HCl immediate-release to KOMBIGLYZE XR, closely monitor glycemic control and adjust the dosage accordingly.

Patients who need 2.5 mg saxagliptin in combination with metformin HCl extended-release may be treated with KOMBIGLYZE XR 2.5 mg/1,000 mg. Patients who need 2.5 mg saxagliptin who are either metformin HCl naive or who require a dose of metformin HCl higher than 1,000 mg should use the individual components.

Gradually titrate the dosage of KOMBIGLYZE XR, as needed, after assessing therapeutic response and tolerability, up to a maximum recommended dosage of KOMBIGLYZE XR (5 mg for saxagliptin and 2,000 mg for metformin HCl extended-release orally once daily).

Inform patients that KOMBIGLYZE XR tablets must be swallowed whole and never crushed, cut, or chewed. Occasionally, the inactive ingredients of KOMBIGLYZE XR will be eliminated in the feces as a soft, hydrated mass that may resemble the original tablet.

If a dose is missed, advise patients not to take an extra dose. Resume treatment with the next dose.

2.2 Recommendations for Dosage and Administration in Renal Impairment

Assess renal function prior to initiation of KOMBIGLYZE XR and then as clinically indicated [see Use in Specific Populations (8.6)].

The recommended dosage of KOMBIGLYZE XR in patients with an estimated glomerular filtration rate (eGFR) greater than or equal to 45 mL/minute/1.73 m2 is the same as the recommended dosage in patients with normal renal function [see Dosage and Administration (2.1)].

In patients taking KOMBIGLYZE XR whose eGFR later falls below 45 mL/minute/1.73 m2, assess the benefit risk of continuing therapy and limit dose of the saxagliptin component to 2.5 mg once daily.

Initiation of KOMBIGLYZE XR in patients with an eGFR between 30 – 45 mL/minute/1.73 m2 is not recommended.

KOMBIGLYZE XR is contraindicated in patients with an eGFR below 30 mL/minute/1.73 m2.

Discontinue KOMBIGLYZE XR if the patient’s eGFR later falls below 30 mL/minute/1.73 m2 [see Contraindications (4) and Warnings and Precautions (5.1)].

2.3 Dosage Modifications with Concomitant Use of Strong CYP3A4/5 Inhibitors

The maximum recommended dosage of KOMBIGLYZE XR is 2.5 mg of saxagliptin and 1,000 mg of metformin HCl given orally once daily when used concomitantly with strong cytochrome P450 3A4/5 (CYP3A4/5) inhibitors (e.g., ketoconazole, atazanavir, clarithromycin, indinavir, itraconazole, nefazodone, nelfinavir, ritonavir, saquinavir, and telithromycin) [see Dosage and Administration (2.1), Drug Interactions (7.1), and Clinical Pharmacology (12.3)].

2.4 Discontinuation for Iodinated Contrast Imaging Procedures

Discontinue KOMBIGLYZE XR at the time of, or prior to, an iodinated contrast imaging procedure in patients with an eGFR less than 60 mL/min/1.73 m2; a history of liver disease, alcoholism or heart failure; or in any patient who will be administered intra-arterial iodinated contrast. Re-evaluate eGFR 48 hours after the imaging procedure; restart KOMBIGLYZE XR if renal function is stable [see Warnings and Precautions (5.1)].

3 DOSAGE FORMS AND STRENGTHS

Extended-Release Tablets:

- 5 mg of saxagliptin and 500 mg of metformin HCl: light brown to brown, biconvex, capsule-shaped, film-coated tablets with “5/500” printed on one side and “4221” printed on the reverse side, in blue ink.
- 5 mg of saxagliptin and 1,000 mg of metformin HCl: pink, biconvex, capsule-shaped, film-coated tablets with “5/1000” printed on one side and “4223” printed on the reverse side, in blue ink.
- 2.5 mg of saxagliptin and 1,000 mg of metformin HCl: pale yellow to light yellow, biconvex, capsule-shaped, film-coated tablets with “2.5/1000” printed on one side and “4222” printed on the reverse side, in blue ink.

4 CONTRAINDICATIONS

KOMBIGLYZE XR is contraindicated in patients with:

- Severe renal impairment (eGFR below 30 mL/min/1.73 m2).
- Acute or chronic metabolic acidosis, including diabetic ketoacidosis. Diabetic ketoacidosis should be treated with insulin.
- A history of a serious hypersensitivity reaction to saxagliptin, metformin HCl, or any of the ingredients in KOMBLIGLYZE XR. Reactions such as anaphylaxis, angioedema, or exfoliative skin conditions have been reported [see Warnings and Precautions (5.6) and Adverse Reactions (6.2)].

5 WARNINGS AND PRECAUTIONS

5.1 Lactic Acidosis

There have been postmarketing cases of metformin-associated lactic acidosis, including fatal cases. These cases had a subtle onset and were accompanied by nonspecific symptoms such as malaise, myalgias, abdominal pain, respiratory distress, or increased somnolence; however, hypothermia, hypotension and resistant bradyarrhythmias have occurred with severe acidosis.

Metformin-associated lactic acidosis was characterized by elevated blood lactate concentrations (>5 mmol/Liter), anion gap acidosis (without evidence of ketonuria or ketonemia), and an increased lactate: pyruvate ratio; metformin plasma levels generally >5 mcg/mL. Metformin decreases liver uptake of lactate increasing lactate blood levels which may increase the risk of lactic acidosis, especially in patients at risk.

If metformin-associated lactic acidosis is suspected, general supportive measures should be instituted promptly in a hospital setting, along with immediate discontinuation of KOMBIGLYZE XR.

In KOMBIGLYZE XR-treated patients with a diagnosis or strong suspicion of lactic acidosis, prompt hemodialysis is recommended to correct the acidosis and remove accumulated metformin (metformin HCl is dialyzable, with a clearance of up to 170 mL/minute under good hemodynamic conditions). Hemodialysis has often resulted in reversal of symptoms and recovery.

Educate patients and their families about the symptoms of lactic acidosis and if these symptoms occur instruct them to discontinue KOMBIGLYZE XR and report these symptoms to their health care provider.

For each of the known and possible risk factors for metformin-associated lactic acidosis, recommendations to reduce the risk of and manage metformin-associated lactic acidosis are provided below:

Renal Impairment: The post-marketing metformin-associated lactic acidosis cases primarily occurred in patients with significant renal impairment. The risk of metformin accumulation and metformin-associated lactic acidosis increases with the severity of renal impairment because metformin is substantially excreted by the kidney. Clinical recommendations based upon the patient’s renal function include [see Clinical Pharmacology (12.3)]:

- Before initiating KOMBIGLYZE XR, obtain an estimated glomerular filtration rate (eGFR).
- KOMBIGLYZE XR is contraindicated in patients with an eGFR less than 30 mL/minute/1.73 m^2 [see Contraindications (4)].
- Initiation of KOMBIGLYZE XR is not recommended in patients with eGFR between 30 and 45 mL/minute/1.73 m^2.
- Obtain an eGFR at least annually in all patients taking KOMBIGLYZE XR. In patients at increased risk for the development of renal impairment (e.g., the elderly), renal function should be assessed more frequently.
- In patients taking KOMBIGLYZE XR whose eGFR later falls below 45 mL/minute/1.73 m^2, assess the benefit and risk of continuing therapy.

Drug Interactions: The concomitant use of KOMBIGLYZE XR with specific drugs may increase the risk of metformin-associated lactic acidosis: those that impair renal function, result in significant hemodynamic change, interfere with acid-base balance or increase metformin accumulation [see Drug Interactions (7)]. Therefore, consider more frequent monitoring of patients.

Age 65 or Greater: The risk of metformin-associated lactic acidosis increases with the patient’s age because elderly patients have a greater likelihood of having hepatic, renal, or cardiac impairment than younger patients. Assess renal function more frequently in elderly patients [see Use in Specific Populations (8.5)].

Radiological Studies with Contrast: Administration of intravascular iodinated contrast agents in metformin-treated patients has led to an acute decrease in renal function and the occurrence of lactic acidosis. Stop KOMBIGLYZE XR at the time of, or prior to, an iodinated contrast imaging procedure in patients with an eGFR between 30 and 60 mL/min/1.73 m^2; in patients with a history of hepatic impairment, alcoholism, or heart failure; or in patients who will be administered intra-arterial iodinated contrast. Re-evaluate eGFR 48 hours after the imaging procedure, and restart KOMBIGLYZE XR if renal function is stable.

Surgery and Other Procedures: Withholding of food and fluids during surgical or other procedures may increase the risk for volume depletion, hypotension and renal impairment. KOMBIGLYZE XR should be temporarily discontinued while patients have restricted food and fluid intake.

Hypoxic States: Several of the post-marketing cases of metformin-associated lactic acidosis occurred in the setting of acute congestive heart failure (particularly when accompanied by hypoperfusion and hypoxemia). Cardiovascular collapse (shock), acute myocardial infarction, sepsis, and other conditions associated with hypoxemia have been associated with lactic acidosis and may also cause prerenal azotemia. When such events occur, discontinue KOMBIGLYZE XR.

Excessive Alcohol Intake: Alcohol potentiates the effect of metformin on lactate metabolism and this may increase the risk of metformin-associated lactic acidosis. Warn patients against excessive alcohol intake while receiving KOMBIGLYZE XR.

Hepatic Impairment: Patients with hepatic impairment have developed with cases of metformin-associated lactic acidosis. This may be due to impaired lactate clearance resulting in higher lactate blood levels. Therefore, avoid use of KOMBIGLYZE XR in patients with clinical or laboratory evidence of hepatic disease.

5.2 Pancreatitis

There have been post-marketing reports of acute pancreatitis in patients taking saxagliptin. In a cardiovascular outcomes trial enrolling participants with established atherosclerotic cardiovascular disease (ASCVD) or multiple risk factors for ASCVD (SAVOR trial), cases of definite acute pancreatitis were confirmed in 17 of 8240 (0.2%) patients receiving saxagliptin compared to 9 of 8173 (0.1%) receiving placebo. Pre-existing risk factors for pancreatitis were identified in 88% (15/17) of those patients receiving saxagliptin and in 100% (9/9) of those patients receiving placebo.

After initiation of KOMBIGLYZE XR, observe patients for signs and symptoms of pancreatitis. If pancreatitis is suspected, promptly discontinue KOMBIGLYZE XR and initiate appropriate management. It is unknown whether patients with a history of pancreatitis are at increased risk for the development of pancreatitis while using KOMBIGLYZE XR.

5.3 Heart Failure

In a cardiovascular outcomes trial enrolling participants with established ASCVD or multiple risk factors for ASCVD (SAVOR trial), more patients randomized to saxagliptin (289/8280, 3.5%) were hospitalized for heart failure compared to patients randomized to placebo (228/8212, 2.8%). In a time-to-first-event analysis the risk of hospitalization for heart failure was higher in the saxagliptin group (estimated Hazard Ratio: 1.27; 95% CI: 1.07, 1.51). Patients with a prior history of heart failure and patients with renal impairment had a higher risk for hospitalization for heart failure, irrespective of treatment assignment.

Consider the risks and benefits of KOMBIGLYZE XR prior to initiating treatment in patients at a higher risk for heart failure. Observe patients for signs and symptoms of heart failure during therapy. Advise patients of the characteristic symptoms of heart failure, and to immediately report such symptoms. If heart failure develops, evaluate and manage according to current standards of care and consider discontinuation of KOMBIGLYZE XR.

5.4 Vitamin B12 Concentrations

In controlled clinical trials of metformin of 29-week duration, a decrease to subnormal levels of previously normal serum vitamin B12 levels, without clinical manifestations, was observed in approximately 7% of patients. Such decrease, possibly due to interference with B12 absorption from the B12-intrinsic factor complex, may be associated with anemia but appears to be rapidly reversible with discontinuation of metformin or vitamin B12 supplementation. Certain individuals (those with inadequate vitamin B12 or calcium intake or absorption) appear to be predisposed to developing subnormal vitamin B12 levels. Measure hematologic parameters on an annual basis and vitamin B12 at 2- to 3-year intervals in patients on KOMBIGLYZE XR and manage any abnormalities [see Adverse Reactions (6.1)].

5.5 Hypoglycemia with Concomitant Use of Insulin or Insulin Secretagogues

Saxagliptin

When saxagliptin was used in combination with insulin or an insulin secretagogue, the incidence of confirmed hypoglycemia was increased over that of placebo used in combination with insulin or an insulin secretagogue [see Adverse Reactions (6.1)]. Therefore, a lower dosage of insulin or an insulin secretagogue may be required to reduce the risk of hypoglycemia when used in combination with KOMBIGLYZE XR.

Metformin HCl

Hypoglycemia does not occur in patients receiving metformin alone under usual circumstances of use, but could occur when caloric intake is deficient, when strenuous exercise is not compensated by caloric supplementation, or during concomitant use with other glucose-lowering agents (such as sulfonylureas and insulin) or ethanol. Elderly, debilitated, or malnourished patients and those with adrenal or pituitary insufficiency or alcohol intoxication are particularly susceptible to hypoglycemic effects. Hypoglycemia may be difficult to recognize in the elderly and in people who are taking beta-adrenergic blocking drugs.

Inform patients using these concomitant medications of the risk of hypoglycemia and educate them on the signs and symptoms of hypoglycemia.

5.6 Hypersensitivity Reactions

There have been post-marketing reports of serious hypersensitivity reactions in patients treated with saxagliptin. These reactions include anaphylaxis, angioedema, and exfoliative skin conditions. Onset of these reactions occurred within the first 3 months after initiation of treatment with saxagliptin, with some reports occurring after the first dose. If a serious hypersensitivity reaction is suspected, discontinue KOMBIGLYZE XR, assess for other potential causes for the event, and institute alternative treatment for diabetes [see Adverse Reactions (6.2)].

Use caution in a patient with a history of angioedema to another dipeptidyl peptidase-4 (DPP4) inhibitor because it is unknown whether such patients will be predisposed to angioedema with KOMBIGLYZE XR.

5.7 Severe and Disabling Arthralgia

There have been post-marketing reports of severe and disabling arthralgia in patients taking DPP4 inhibitors. The time to onset of symptoms following initiation of drug therapy varied from one day to years. Patients experienced relief of symptoms upon discontinuation of the medication. A subset of patients experienced a recurrence of symptoms when restarting the same drug or a different DPP4 inhibitor. Consider DPP4 inhibitors as a possible cause for severe joint pain and discontinue drug if appropriate.

5.8 Bullous Pemphigoid

Postmarketing cases of bullous pemphigoid requiring hospitalization have been reported with DPP 4 inhibitor use. In reported cases, patients typically recovered with topical or systemic immunosuppressive treatment and discontinuation of the DPP 4 inhibitor. Tell patients to report development of blisters or erosions while receiving KOMBIGLYZE XR. If bullous pemphigoid is suspected, KOMBIGLYZE XR should be discontinued and referral to a dermatologist should be considered for diagnosis and appropriate treatment.

6 ADVERSE REACTIONS

The following serious adverse reactions are described below or elsewhere in the prescribing information:

- Lactic Acidosis [see Boxed Warning and Warnings and Precautions (5.1)]
- Pancreatitis [see Warnings and Precautions (5.2)]
- Heart Failure [see Warnings and Precautions (5.3)]
- Vitamin B12 Concentrations [see Warnings and Precautions (5.4)]
- Hypoglycemia with Concomitant Use of Insulin or Insulin Secretagogues [see Warnings and Precautions (5.5)]
- Hypersensitivity Reactions [see Warnings and Precautions (5.6)]
- Severe and disabling arthralgia [see Warnings and Precautions (5.7)]
- Bullous pemphigoid [see Warnings and Precautions (5.8)]

6.1 Clinical Trials Experience

Because clinical trials are conducted under widely varying conditions, adverse reaction rates observed in the clinical trials of a drug cannot be directly compared to rates in the clinical trials of another drug and may not reflect the rates observed in practice.

Adverse Reactions in Placebo-Controlled Trials in Adults with Type 2 Diabetes Mellitus

ADVERSE REACTIONS

Metformin HCl

In placebo-controlled monotherapy trials of metformin HCl extended-release, diarrhea and nausea/vomiting were reported in >5% of metformin-treated patients and more commonly than in placebo-treated patients (9.6% versus 2.6% for diarrhea and 6.5% versus 1.5% for nausea/vomiting). Diarrhea led to discontinuation of trial medication in 0.6% of the patients treated with metformin HCl extended-release.

ADVERSE REACTIONS

Saxagliptin

The data in Table 1 are derived from a pool of 5 placebo-controlled clinical trials [see Clinical Studies (14)]. These data shown in the table reflect exposure of 882 patients to saxagliptin and a mean duration of exposure to saxagliptin of 21 weeks. The mean age of these patients was 55 years, 1.4% were 75 years or older and 48.4% were male. The population was 67.5% White, 4.6% Black or African American, 17.4% Asian, 10.5% other races and 9.8% were of Hispanic or Latino ethnicity. At baseline the population had diabetes for an average of 5.2 years and a mean HbA1c of 8.2%. Baseline estimated renal function was normal or mildly impaired (eGFR ≥60mL/min/1.73m^2) in 91% of these patients.

Table 1 shows common adverse reactions, excluding hypoglycemia, associated with the use of saxagliptin. These adverse reactions occurred more commonly on saxagliptin than on placebo and occurred in at least 5% of patients treated with saxagliptin.

Table 1: Adverse Reactions in Placebo-Controlled Trials [The 5 placebo-controlled trials include two monotherapy trials and one add-on combination therapy trial with each of the following: metformin HCl, thiazolidinedione, or glyburide. Table shows 24-week data regardless of glycemic rescue.] Reported in ≥5% of Patients Treated with Saxagliptin 5 mg and More Commonly than in Patients Treated with Placebo
 | % of Patients
 | Saxagliptin 5 mg N=882 | Placebo N=799
Upper respiratory tract infection | 7.7 | 7.6
Urinary tract infection | 6.8 | 6.1
Headache | 6.5 | 5.9

In patients treated with saxagliptin 2.5 mg, headache (6.5%) was the only adverse reaction reported at a rate ≥5% and more commonly than in patients treated with placebo.

In the add-on to TZD trial, the incidence of peripheral edema was higher for saxagliptin 5 mg versus placebo (8.1% and 4.3%, respectively). The incidence of peripheral edema for saxagliptin 2.5 mg was 3.1%. None of the reported adverse reactions of peripheral edema resulted in trial drug discontinuation. Rates of peripheral edema for saxagliptin 2.5 mg and saxagliptin 5 mg versus placebo were 3.6% and 2% versus 3% given as monotherapy, 2.1% and 2.1% versus 2.2% given as add-on therapy to metformin HCl, and 2.4% and 1.2% versus 2.2% given as add-on therapy to glyburide.

The incidence rate of fractures was 1.0 and 0.6 per 100 patient-years, respectively, for saxagliptin (pooled analysis of 2.5 mg, 5 mg, and 10 mg) and placebo. The 10 mg saxagliptin dosage is not an approved dosage. The incidence rate of fracture events in patients who received saxagliptin did not increase over time. Causality has not been established and nonclinical studies have not demonstrated adverse effects of saxagliptin on bone.

An event of thrombocytopenia, consistent with a diagnosis of idiopathic thrombocytopenic purpura, was observed in the clinical program. The relationship of this event to saxagliptin is not known.

Discontinuation of therapy due to adverse reactions occurred in 2.2%, 3.3%, and 1.8% of patients receiving saxagliptin 2.5 mg, saxagliptin 5 mg, and placebo, respectively. The most common adverse reactions (reported in at least 2 patients treated with saxagliptin 2.5 mg or at least 2 patients treated with saxagliptin 5 mg) associated with premature discontinuation of therapy included lymphopenia (0.1% and 0.5% versus 0%, respectively), rash (0.2% and 0.3% versus 0.3%), blood creatinine increased (0.3% and 0% versus 0%), and blood creatine phosphokinase increased (0.1% and 0.2% versus 0%).

Adverse Reactions with Concomitant Use with Insulin

In the add-on to insulin trial [see Clinical Studies (14.1)], the incidence of adverse events, including serious adverse events and discontinuations due to adverse events, was similar between saxagliptin and placebo, except for confirmed hypoglycemia [see Adverse Reactions (6.1)].

Adverse Reactions Associated with Saxagliptin Coadministered with Metformin HCl Immediate-Release in Treatment-Naive Patients with Type 2 Diabetes Mellitus

Table 2 shows the adverse reactions reported (regardless of investigator assessment of causality) in ≥5% of patients participating in an additional 24-week, active-controlled trial of coadministered saxagliptin and metformin HCl in treatment-naive patients.

Table 2: Coadministration of Saxagliptin and Metformin HCl Immediate-Release in Treatment-Naive Patients: Adverse Reactions Reported in ≥5% of Patients Treated with Combination Therapy of Saxagliptin 5 mg Plus Metformin HCl Immediate-Release (and More Commonly than in Patients Treated with Metformin HCl Immediate-Release Alone
 | Number (%) of Patients
 | Saxagliptin 5 mg + Metformin HCl [Metformin HCl immediate-release was initiated at a starting dose of 500 mg daily and titrated up to a maximum of 2,000 mg daily.] N=320 | Placebo + MetforminHCl N=328
Headache | 24 (7.5) | 17 (5.2)
Nasopharyngitis | 22 (6.9) | 13 (4.0)

In patients treated with the combination of saxagliptin and metformin HCl immediate-release, either as saxagliptin add-on to metformin HCl immediate-release therapy or as coadministration in treatment-naive patients, diarrhea was the only gastrointestinal-related event that occurred with an incidence ≥5% in any treatment group in both trials. In the saxagliptin add-on to metformin HCl immediate-release trial, the incidence of diarrhea was 9.9%, 5.8%, and 11.2% in the saxagliptin 2.5 mg, 5 mg, and placebo groups, respectively. When saxagliptin and metformin HCl immediate-release were coadministered in treatment-naive patients, the incidence of diarrhea was 6.9% in the saxagliptin 5 mg + metformin HCl immediate-release group and 7.3% in the placebo + metformin HCl immediate-release group.

Hypoglycemia

In the saxagliptin clinical trials, adverse reactions of hypoglycemia were based on all reports of hypoglycemia. A concurrent glucose measurement was not required or was normal in some patients. Therefore, it is not possible to conclusively determine that all these reports reflect true hypoglycemia.

The incidence of reported hypoglycemia for saxagliptin 2.5 mg and saxagliptin 5 mg versus placebo given as monotherapy was 4% and 5.6% versus 4.1%, respectively. In the add-on to metformin HCl immediate-release trial, the incidence of reported hypoglycemia was 7.8% with saxagliptin 2.5 mg, 5.8% with saxagliptin 5 mg, and 5% with placebo. When saxagliptin and metformin HCl immediate-release were coadministered in treatment-naive patients, the incidence of reported hypoglycemia was 3.4% in patients given saxagliptin 5 mg + metformin HCl immediate-release and 4% in patients given placebo + metformin HCl immediate-release.

In the active-controlled trial comparing add-on therapy with saxagliptin 5 mg to glipizide in patients inadequately controlled on metformin HCl alone, the incidence of reported hypoglycemia was 3% (19 events in 13 patients) with saxagliptin 5 mg versus 36.3% (750 events in 156 patients) with glipizide. Confirmed symptomatic hypoglycemia (accompanying fingerstick blood glucose ≤50 mg/dL) was reported in none of the saxagliptin-treated patients and in 35 glipizide-treated patients (8.1%) (p<0.0001).

In the saxagliptin add-on to insulin trial, the overall incidence of reported hypoglycemia was 18.4% for saxagliptin 5 mg and 19.9% for placebo. However, the incidence of confirmed symptomatic hypoglycemia (accompanying fingerstick blood glucose ≤50 mg/dL) was higher with saxagliptin 5 mg (5.3%) versus placebo (3.3%). Among the patients using insulin in combination with metformin HCl, the incidence of confirmed symptomatic hypoglycemia was 4.8% with saxagliptin versus 1.9% with placebo.

In the saxagliptin add-on to metformin HCl plus sulfonylurea trial, the overall incidence of reported hypoglycemia was 10.1% for saxagliptin 5 mg and 6.3% for placebo. Confirmed hypoglycemia was reported in 1.6% of the saxagliptin-treated patients and in none of the placebo-treated patients [see Warnings and Precautions (5.5)].

Hypersensitivity Reactions

Saxagliptin

Hypersensitivity reactions, such as urticaria and facial edema in the 5-trial pooled analysis up to Week 24 were reported in 1.5%, 1.5%, and 0.4% of patients who received saxagliptin 2.5 mg, saxagliptin 5 mg, and placebo, respectively. None of these events in patients who received saxagliptin required hospitalization or were reported as life-threatening by the investigators. One saxagliptin-treated patient in this pooled analysis discontinued due to generalized urticaria and facial edema.

Renal Impairment

In the SAVOR trial, adverse reactions related to renal impairment, including laboratory changes (i.e., doubling of serum creatinine compared with baseline and serum creatinine >6 mg/dL), were reported in 5.8% (483/8280) of saxagliptin-treated patients and 5.1% (422/8212) of placebo-treated patients. The most frequently reported adverse reactions included renal impairment (2.1% vs. 1.9%), acute renal failure (1.4% vs. 1.2%), and renal failure (0.8% vs. 0.9%), in the saxagliptin versus placebo groups, respectively. From baseline to the end of treatment, there was a mean decrease in eGFR of 2.5 mL/min/1.73m^2 for saxagliptin-treated patients and a mean decrease of 2.4 mL/min/1.73m^2 for placebo-treated patients. More patients randomized to saxagliptin (421/5227, 8.1%) compared to patients randomized to placebo (344/5073, 6.8%) had downward shifts in eGFR from >50 mL/min/1.73 m^2 (i.e., normal or mild renal impairment) to ≤50 mL/min/1.73 m^2 (i.e., moderate or severe renal impairment). The proportions of patients with renal adverse reactions increased with worsening baseline renal function and increased age, regardless of treatment assignment.

Infections

Saxagliptin

In the unblinded, controlled, clinical trial database for saxagliptin to date, there have been 6 (0.12%) reports of tuberculosis among the 4959 saxagliptin-treated patients (1.1 per 1000 patient-years) compared to no reports of tuberculosis among the 2868 comparator-treated patients. Two of these six cases were confirmed with laboratory testing. The remaining cases had limited information or had presumptive diagnoses of tuberculosis. None of the six cases occurred in the United States or in Western Europe. One case occurred in Canada in a patient originally from Indonesia who had recently visited Indonesia. The duration of treatment with saxagliptin until report of tuberculosis ranged from 144 to 929 days. Post-treatment lymphocyte counts were consistently within the reference range for four cases. One patient had lymphopenia prior to initiation of saxagliptin that remained stable throughout saxagliptin treatment. The final patient had an isolated lymphocyte count below normal approximately four months prior to the report of tuberculosis. There have been no spontaneous reports of tuberculosis associated with saxagliptin use. Causality has not been established and there are too few cases to date to determine whether tuberculosis is related to saxagliptin use.

There has been one case of a potential opportunistic infection in the unblinded, controlled clinical trial database to date in a saxagliptin-treated patient who developed suspected foodborne fatal salmonella sepsis after approximately 600 days of saxagliptin therapy. There have been no spontaneous reports of opportunistic infections associated with saxagliptin use.

Vital Signs

Saxagliptin

No clinically meaningful changes in vital signs have been observed in patients treated with saxagliptin alone or in combination with metformin HCl.

Laboratory Tests

Absolute Lymphocyte Counts

Saxagliptin

There was a dose-related mean decrease in absolute lymphocyte count observed with saxagliptin. From a baseline mean absolute lymphocyte count of approximately 2200 cells/microL, mean decreases of approximately 100 and 120 cells/microL with saxagliptin 5 mg and 10 mg, respectively, relative to placebo were observed at 24 weeks in a pooled analysis of five placebo-controlled clinical trials. Similar effects were observed when saxagliptin 5 mg and metformin HCl were coadministered in treatment-naive patients compared to placebo and metformin HCl. There was no difference observed for saxagliptin 2.5 mg relative to placebo. The proportion of patients who were reported to have a lymphocyte count ≤750 cells/microL was 0.5%, 1.5%, 1.4%, and 0.4% in the saxagliptin 2.5 mg, 5 mg, 10 mg, and placebo groups, respectively. In most patients, recurrence was not observed with repeated exposure to saxagliptin although some patients had recurrent decreases upon rechallenge that led to discontinuation of saxagliptin. The decreases in lymphocyte count were not associated with clinically relevant adverse reactions. The 10 mg saxagliptin dosage is not an approved dosage.

In the SAVOR trial mean decreases of approximately 84 cells/microL with saxagliptin relative to placebo was observed. The proportion of patients who experienced a decrease in lymphocyte counts to a count of ≤750 cells/microL was 1.6% (136/8280) and 1.0% (78/8212) on saxagliptin and placebo, respectively.

The clinical significance of this decrease in lymphocyte count relative to placebo is not known. When clinically indicated, such as in settings of unusual or prolonged infection, lymphocyte count should be measured. The effect of saxagliptin on lymphocyte counts in patients with lymphocyte abnormalities (e.g., human immunodeficiency virus) is unknown.

Vitamin B12 Concentrations

Metformin HCl

In metformin clinical trials of 29 week duration, a decrease to subnormal levels of previously normal serum vitamin B12 levels was observed in approximately 7% of patients.

6.2 Postmarketing Experience

Additional adverse reactions have been identified during post-approval use of KOMBIGLYZE XR, saxagliptin, or metformin HCl. Because these reactions are reported voluntarily from a population of uncertain size, it is generally not possible to reliably estimate their frequency or establish a causal relationship to drug exposure.

Saxagliptin

- Gastrointestinal Disorders: Pancreatitis
- Immune System Disorders: Hypersensitivity reactions including anaphylaxis, angioedema, and exfoliative skin conditions
- Musculoskeletal and Connective Tissue Disorders: Rhabdomyolysis, Severe and disabling arthralgia
- Skin and Subcutaneous Tissue Disorders: Bullous pemphigoid

Metformin HCl

- Hepatobiliary Disorders: Cholestatic, hepatocellular, and mixed hepatocellular liver injury

7 DRUG INTERACTIONS

7.1 Strong Inhibitors of CYP3A4/5 Enzymes

Ketoconazole significantly increased saxagliptin exposure. Similar significant increases in plasma concentrations of saxagliptin are anticipated with other strong CYP3A4/5 inhibitors (e.g., atazanavir, clarithromycin, indinavir, itraconazole, nefazodone, nelfinavir, ritonavir, saquinavir, and telithromycin). The dose of KOMBIGLYZE XR should be limited to 2.5 mg of saxagliptin when coadministered with a strong CYP3A4/5 inhibitor [see Dosage and Administration (2.3) and Clinical Pharmacology (12.3) ].

7.2 Carbonic Anhydrase Inhibitors

Topiramate or other carbonic anhydrase inhibitors (e.g., zonisamide, acetazolamide or dichlorphenamide) frequently causes a decrease in serum bicarbonate and induce non-anion gap, hyperchloremic metabolic acidosis. Concomitant use of these drugs with KOMBIGLYZE XR may increase the risk for lactic acidosis.

7.3 Drugs that Reduce Metformin Clearance

Concomitant use of drugs that interfere with common renal tubular transport systems involved in the renal elimination of metformin (e.g., organic cationic transporter-2 [OCT2]/multidrug and toxin extrusion [MATE] inhibitors such as ranolazine, vandetanib, dolutegravir, and cimetidine) could increase systemic exposure to metformin and may increase the risk for lactic acidosis [see Clinical Pharmacology (12.3)]. Consider the benefits and risks of concomitant use.

7.4 Alcohol

Alcohol is known to potentiate the effect of metformin on lactate metabolism. Warn patients against excessive alcohol intake while receiving KOMBIGLYZE XR.

7.5 Insulin or Insulin Secretagogues

Insulin and insulin secretagogues are known to cause hypoglycemia. Concomitant use of KOMBIGLYZE XR with insulin or an insulin secretagogue may require lower dosages of insulin or the insulin secretagogue to reduce the risk of hypoglycemia [see Warnings and Precautions (5.5)].

7.6 Drugs Affecting Glycemic Control

Certain drugs tend to produce hyperglycemia and may lead to loss of glycemic control. These medications include the thiazides and other diuretics, corticosteroids, phenothiazines, thyroid products, estrogens, oral contraceptives, phenytoin, nicotinic acid, sympathomimetics, calcium channel blocking drugs, and isoniazid. When such drugs are administered to a patient receiving KOMBIGLYZE XR, observe the patient closely for loss of blood glucose control. When such drugs are withdrawn from a patient receiving KOMBIGLYZE XR, observe the patient closely for hypoglycemia.

8 USE IN SPECIFIC POPULATIONS

8.1 Pregnancy

Risk Summary

Limited available data with KOMBIGLYZE XR or saxagliptin in pregnant women are not sufficient to determine a drug-associated risk for major birth defects and miscarriage. Published trials with metformin use during pregnancy have not reported a clear association with metformin and major birth defect or miscarriage risk [see Data].

No adverse developmental effects independent of maternal toxicity were observed when saxagliptin and metformin were administered separately or in combination to pregnant rats and rabbits during the period of organogenesis [see Data].

The estimated background risk of major birth defects is 6 to 10% in women with pre-gestational diabetes with an HbA1c greater than 7 and has been reported to be as high as 20 to 25% in women with an HbA1c greater than 10. The estimated background risk of miscarriage for the indicated population is unknown. In the U.S. general population, the estimated background risk of major birth defects and miscarriage in clinically recognized pregnancies is 2 to 4% and 15 to 20%, respectively.

Clinical Considerations

Disease-associated maternal and/or embryo/fetal risk

Poorly controlled diabetes in pregnancy increases the maternal risk for diabetic ketoacidosis, preeclampsia, spontaneous abortions, preterm delivery, still birth and delivery complications. Poorly controlled diabetes increases the fetal risk for major birth defects, stillbirth, and macrosomia related morbidity.

Data

Animal Data

TERATOGENIC EFFECTS

Saxagliptin

In embryo-fetal development studies, saxagliptin was administered to pregnant rats and rabbits during the period of organogenesis, corresponding to the first trimester of human pregnancy. No adverse developmental effects were observed in either species at exposures 1503- and 152-times the 5 mg clinical dose in rats and rabbits, respectively, based on AUC. Saxagliptin crosses the placenta into the fetus following dosing in pregnant rats.

In a prenatal and postnatal development study, no adverse developmental effects were observed in maternal rats administered saxagliptin from gestation day 6 through lactation day 21 at exposures up to 470-times the 5 mg clinical dose, based on AUC.

TERATOGENIC EFFECTS

Metformin HCI

Metformin hydrochloride did not cause adverse developmental effect when administered to pregnant Sprague Dawley rats and rabbits up to 600 mg/kg/day during the period of organogenesis. This represents an exposure of about 2- and 6-times a 2,000 mg clinical dose based on body surface area (mg/m^2) for rats and rabbits, respectively.

Saxagliptin and Metformin

Saxagliptin and metformin coadministered to pregnant rats and rabbits during the period of organogenesis did not result in adverse developmental effects considered clinically relevant in either species. Doses tested in rats provided exposure up to 100- and 10-times clinical exposure, and doses tested in rabbits provided exposure up to 249- and 1-times clinical exposure relative to the clinical dose of 5 mg saxagliptin and 2,000 mg metformin. Minor skeletal abnormalities associated with maternal toxicity were observed in rats. In rabbits, coadministration was poorly tolerated in a subset of mothers (12 of 30), resulting in death, moribundity, or abortion. However, among surviving mothers with evaluable litters, maternal toxicity was limited to marginal reductions in body weight over the course of gestation days 21 to 29, associated with fetal body weight decrements of 7%, and a low incidence of delayed ossification of the fetal hyoid bone.

8.2 Lactation

Risk Summary

There is no information regarding the presence of KOMBIGLYZE XR or saxagliptin in human milk, the effects on the breastfed infant, or the effects on milk production. Limited published studies report that metformin is present in human milk [see Data]. However, there is insufficient information on the effects of metformin on the breastfed infant and no available information on the effects of metformin on milk production. Saxagliptin is present in the milk of lactating rats [see Data].

The developmental and health benefits of breastfeeding should be considered along with the mother’s clinical need for KOMBIGLYZE XR and any potential adverse effects on the breastfed child from KOMBIGLYZE XR or from the underlying maternal condition.

Data

Human Data

Published clinical lactation studies report that metformin is present in human milk which resulted in infant doses approximately 0.11% to 1% of the maternal weight-adjusted dosage and a milk/plasma ratio ranging between 0.13 and 1. However, the studies were not designed to definitely establish the risk of use of metformin during lactation because of small sample size and limited adverse event data collected in infants.

Animal Data

No studies in lactating animals have been conducted with the combined components of KOMBIGLYZE XR. In studies performed with the individual components, both saxagliptin and metformin are secreted in the milk of lactating rats. Saxagliptin is secreted in the milk of lactating rats at approximately a 1:1 ratio with plasma drug concentrations.

8.4 Pediatric Use

The safety and effectiveness of KOMBIGLYZE XR as an adjunct to diet and exercise to improve glycemic control in patients with type 2 diabetes mellitus have not been established in pediatric patients.

Effectiveness of saxagliptin was not demonstrated in a 26-week, placebo-controlled, double-blind randomized clinical trial with a 26-week safety extension (NCT03199053) in 164 pediatric patients aged 10 to 17 years with inadequately controlled type 2 diabetes mellitus.

8.5 Geriatric Use

KOMBIGLYZE XR

Elderly patients are more likely to have decreased renal function. Assess renal function more frequently in the elderly [see Warnings and Precautions (5.1) and Clinical Pharmacology (12.3)].

Saxagliptin

In the seven, double-blind, controlled clinical safety and efficacy trials of saxagliptin, a total of 4751 (42.0%) of the 11301 patients randomized to saxagliptin were 65 years and over, and 1210 (10.7%) were 75 years and over. No overall differences in safety or effectiveness were observed between patients 65 years of age and older and younger adult patients.

Metformin HCI

Controlled clinical trials of metformin did not include sufficient numbers of elderly patients to determine whether they respond differently than younger patients. In general, dose selection for an elderly patient should be cautious, usually starting at the low end of the dosing range, reflecting the greater frequency of decreased hepatic, renal, or cardiac function, and of concomitant disease or other drug therapy and the higher risk of lactic acidosis. Assess renal function more frequently in elderly patients [see Warnings and Precautions (5.1)].

8.6 Renal Impairment

Saxagliptin

In a 12-week randomized placebo-controlled trial, saxagliptin 2.5 mg was administered to 85 patients with moderate (n=48) or severe (n=18) renal impairment or end-stage renal disease (ESRD) (n=19) [see Clinical Studies (14)]. The incidence of adverse events, including serious adverse events and discontinuations due to adverse events, was similar between saxagliptin and placebo. The overall incidence of reported hypoglycemia was 20% among patients treated with saxagliptin 2.5 mg and 22% among patients treated with placebo. Four saxagliptin-treated patients (4.7%) and three placebo-treated patients (3.5%) reported at least one episode of confirmed symptomatic hypoglycemia (accompanying fingerstick glucose ≤50 mg/dL).

Metformin HCI

Metformin is substantially excreted by the kidney, and the risk of metformin accumulation and lactic acidosis increases with the degree of renal impairment. KOMBIGLYZE XR is contraindicated in severe renal impairment, patients with an estimated glomerular filtration rate (eGFR) below 30 mL/min/1.73 m^2 [see Dosage and Administration (2.2), Contraindications (4), Warnings and Precautions (5.1) and Clinical Pharmacology (12.3)].

8.7 Hepatic Impairment

Use of metformin in patients with hepatic impairment has been associated with some cases of lactic acidosis. KOMBIGLYZE XR is not recommended in patients with hepatic impairment [see Warnings and Precautions (5.1)].

10 OVERDOSAGE

OVERDOSAGE

Saxagliptin

In a controlled clinical trial, once-daily, orally administered saxagliptin in healthy subjects at doses up to 400 mg daily for 2 weeks (80-times the MRHD) had no dose-related clinical adverse reactions and no clinically meaningful effect on QTc interval or heart rate.

In the event of an overdose, initiate appropriate supportive treatment as dictated by the patient’s clinical status. Saxagliptin and its active metabolite are removed by hemodialysis (23% of dose over 4 hours). Contact the Poison Help line (1-800-222-1222) or a medical toxicologist for additional overdosage management recommendations.

OVERDOSAGE

Metformin HCI

Overdose of metformin HCl has occurred, including ingestion of amounts greater than 50 grams. Hypoglycemia was reported in approximately 10% of cases, but no causal association with metformin HCl has been established. Lactic acidosis has been reported in approximately 32% of metformin overdose cases [see Warnings and Precautions (5.1)]. Metformin is dialyzable with a clearance of up to 170 mL/min under good hemodynamic conditions. Therefore, hemodialysis may be useful for removal of accumulated drug from patients in whom metformin overdosage is suspected.

11 DESCRIPTION

KOMBIGLYZE XR (saxagliptin and metformin HCl extended-release) tablets contain two oral antihyperglycemic medications used in the management of type 2 diabetes mellitus: saxagliptin and metformin HCl.

DESCRIPTION

Saxagliptin

Saxagliptin is an orally active inhibitor of the dipeptidyl-peptidase-4 (DPP4) enzyme.

Saxagliptin monohydrate is described chemically as (1S,3S,5S)-2-[(2S)-2-Amino-2-(3-hydroxytricyclo[3.3.1.^13,7]dec-1-yl)acetyl]-2-azabicyclo[3.1.0]hexane-3-carbonitrile, monohydrate or (1S,3S,5S)-2-[(2S)-2-Amino-2-(3-hydroxyadamantan-1-yl)acetyl]-2-azabicyclo[3.1.0]hexane-3-carbonitrile hydrate. The empirical formula is C18H25N3O2•H2O and the molecular weight is 333.43. The structural formula is:

Saxagliptin monohydrate is a white to light yellow or light brown, non-hygroscopic, crystalline powder. It is sparingly soluble in water at 24°C ± 3°C, slightly soluble in ethyl acetate, and soluble in methanol, ethanol, isopropyl alcohol, acetonitrile, acetone, and polyethylene glycol 400 (PEG 400).

DESCRIPTION

Metformin HCl

Metformin HCl (N,N-dimethylimidodicarbonimidic diamide HCl) is a white to off-white crystalline compound with a molecular formula of C4H11N5 • HCl and a molecular weight of 165.63. Metformin HCl is freely soluble in water, slightly soluble in alcohol, and is practically insoluble in acetone, ether, and chloroform. The pKa of metformin is 12.4. The pH of a 1% aqueous solution of metformin HCl is 6.68. The structural formula is:

DESCRIPTION

KOMBIGLYZE XR

KOMBIGLYZE XR is available for oral administration as tablets containing either 5.58 mg saxagliptin HCl (anhydrous) equivalent to 5 mg saxagliptin and 500 mg metformin HCl (KOMBIGLYZE XR 5 mg/500 mg), or 5.58 mg saxagliptin HCl (anhydrous) equivalent to 5 mg saxagliptin and 1,000 mg metformin HCl (KOMBIGLYZE XR 5 mg/1,000 mg), or 2.79 mg saxagliptin HCl (anhydrous) equivalent to 2.5 mg saxagliptin and 1,000 mg metformin HCl (KOMBIGLYZE XR 2.5 mg/1,000 mg). Each film-coated tablet of KOMBIGLYZE XR contains the following inactive ingredients: carboxymethylcellulose sodium, hypromellose 2208, and magnesium stearate. The 5 mg/500 mg strength tablet of KOMBIGLYZE XR also contains microcrystalline cellulose and hypromellose 2910. In addition, the film coatings contain the following inactive ingredients: polyvinyl alcohol, polyethylene glycol 3350, titanium dioxide, talc, and iron oxides.

DESCRIPTION

The biologically inert components of the tablet may occasionally remain intact during gastrointestinal transit and will be eliminated in the feces as a soft, hydrated mass.

12 CLINICAL PHARMACOLOGY

12.1 Mechanism of Action

MECHANISM OF ACTION

KOMBIGLYZE XR

KOMBIGLYZE XR contains two antihyperglycemic medications: saxagliptin, a dipeptidyl-peptidase-4 (DPP4) inhibitor, and metformin HCl, a biguanide.

MECHANISM OF ACTION

Saxagliptin

Increased concentrations of the incretin hormones such as glucagon-like peptide-1 (GLP-1) and glucose-dependent insulinotropic polypeptide (GIP) are released into the bloodstream from the small intestine in response to meals. These hormones cause insulin release from the pancreatic beta cells in a glucose-dependent manner but are inactivated by the DPP4 enzyme within minutes. GLP-1 also lowers glucagon secretion from pancreatic alpha cells, reducing hepatic glucose production. In patients with type 2 diabetes mellitus, concentrations of GLP-1 are reduced but the insulin response to GLP-1 is preserved. Saxagliptin is a competitive DPP4 inhibitor that slows the inactivation of the incretin hormones, thereby increasing their bloodstream concentrations and reducing fasting and postprandial glucose concentrations in a glucose-dependent manner in patients with type 2 diabetes mellitus.

MECHANISM OF ACTION

Metformin HCl

Metformin improves glucose tolerance in patients with type 2 diabetes mellitus, lowering both basal and postprandial plasma glucose. Metformin decreases hepatic glucose production, decreases intestinal absorption of glucose, and improves insulin sensitivity by increasing peripheral glucose uptake and utilization. Unlike sulfonylureas, metformin does not produce hypoglycemia in patients with type 2 diabetes mellitus or in healthy subjects except in unusual circumstances [see Warnings and Precautions (5.5)] and does not cause hyperinsulinemia. With metformin therapy, insulin secretion remains unchanged while fasting insulin levels and day-long plasma insulin response may actually decrease.

12.2 Pharmacodynamics

PHARMACODYNAMICS

Saxagliptin

In patients with type 2 diabetes mellitus, administration of saxagliptin inhibits DPP4 enzyme activity for a 24-hour period. After an oral glucose load or a meal, this DPP4 inhibition resulted in a 2- to 3-fold increase in circulating levels of active GLP-1 and GIP, decreased glucagon concentrations, and increased glucose-dependent insulin secretion from pancreatic beta cells. The rise in insulin and decrease in glucagon were associated with lower fasting glucose concentrations and reduced glucose excursion following an oral glucose load or a meal.

PHARMACODYNAMICS

Saxagliptin

In a randomized, double-blind, placebo-controlled, 4-way crossover, active comparator trial using moxifloxacin in 40 healthy subjects, saxagliptin was not associated with clinically meaningful prolongation of the QTc interval or heart rate at daily doses up to 40 mg (8-times the MRHD).

12.3 Pharmacokinetics

PHARMACOKINETICS

KOMBIGLYZE XR

Bioequivalence and food effect of KOMBIGLYZE XR was characterized under low calorie diet. The low calorie diet consisted of 324 kcal with meal composition that contained 11.1% protein, 10.5% fat, and 78.4% carbohydrate. The results of bioequivalence studies in healthy subjects demonstrated that KOMBIGLYZE XR combination tablets are bioequivalent to coadministration of corresponding doses of saxagliptin (ONGLYZA) and metformin HCl extended-release as individual tablets under fed conditions.

Saxagliptin

The pharmacokinetics of saxagliptin and its active metabolite, 5-hydroxy saxagliptin were similar in healthy subjects and in patients with type 2 diabetes mellitus. The Cmax and AUC values of saxagliptin and its active metabolite increased proportionally in the 2.5 to 400 mg dose range. Following a 5 mg single oral dose of saxagliptin to healthy subjects, the mean plasma AUC values for saxagliptin and its active metabolite were 78 ng•h/mL and 214 ng•h/mL, respectively. The corresponding plasma Cmax values were 24 ng/mL and 47 ng/mL, respectively. The average variability (%CV) for AUC and Cmax for both saxagliptin and its active metabolite was less than 25%.

No appreciable accumulation of either saxagliptin or its active metabolite was observed with repeated once-daily dosing at any dose level. No dose- and time-dependence were observed in the clearance of saxagliptin and its active metabolite over 14 days of once-daily dosing with saxagliptin at doses ranging from 2.5 to 400 mg.

Metformin HCl

Metformin extended-release Cmax is achieved with a median value of 7 hours and a range of 4 to 8 hours. At steady state, the AUC and Cmax are less than dose proportional for metformin extended-release within the range of 500 to 2,000 mg. After repeated administration of metformin extended-release, metformin did not accumulate in plasma. Metformin is excreted unchanged in the urine and does not undergo hepatic metabolism. Peak plasma levels of metformin extended-release tablets are approximately 20% lower compared to the same dose of metformin immediate-release tablets, however, the extent of absorption (as measured by AUC) is similar between extended-release tablets and immediate-release tablets.

Absorption

Saxagliptin

The median time to maximum concentration (Tmax) following the 5 mg once daily dose was 2 hours for saxagliptin and 4 hours for its active metabolite.

Metformin HCl

Following a single oral dose of metformin extended-release, Cmax is achieved with a median value of 7 hours and a range of 4 to 8 hours.

Effect of Food

Saxagliptin

Administration with a high-fat meal resulted in an increase in Tmax of saxagliptin by approximately 20 minutes as compared to fasted conditions. There was a 27% increase in the AUC of saxagliptin when given with a meal as compared to fasted conditions. Food has no significant effect on the pharmacokinetics of saxagliptin when administered as KOMBIGLYZE XR combination tablets.

Metformin HCl

Although the extent of metformin absorption (as measured by AUC) from the metformin extended-release tablet increased by approximately 50% when given with food, there was no effect of food on Cmax and Tmax of metformin. Both high and low fat meals had the same effect on the pharmacokinetics of metformin extended-release. Food has no significant effect on the pharmacokinetics of metformin when administered as KOMBIGLYZE XR combination tablets.

Distribution

Saxagliptin

The in vitro protein binding of saxagliptin and its active metabolite in human serum is negligible. Therefore, changes in blood protein levels in various disease states (e.g., renal or hepatic impairment) are not expected to alter the disposition of saxagliptin.

Metformin HCl

Distribution studies with extended-release metformin have not been conducted; however, the apparent volume of distribution (V/F) of metformin following single oral doses of immediate-release metformin 850 mg averaged 654 ± 358 L. Metformin is negligibly bound to plasma proteins, in contrast to sulfonylureas, which are more than 90% protein bound. Metformin partitions into erythrocytes, most likely as a function of time. Metformin is negligibly bound to plasma proteins and is, therefore, less likely to interact with highly protein-bound drugs such as salicylates, sulfonamides, chloramphenicol, and probenecid, as compared to the sulfonylureas, which are extensively bound to serum proteins.

Elimination

Metabolism

Saxagliptin

The metabolism of saxagliptin is primarily mediated by cytochrome P450 3A4/5 (CYP3A4/5). The major metabolite of saxagliptin is also a DPP4 inhibitor, which is one-half as potent as saxagliptin. Therefore, strong CYP3A4/5 inhibitors and inducers will alter the pharmacokinetics of saxagliptin and its active metabolite [see Drug Interactions (7.1)].

Metformin HCl

Intravenous single-dose studies in healthy subjects demonstrate that metformin is excreted unchanged in the urine and does not undergo hepatic metabolism (no metabolites have been identified in humans) or biliary excretion.

Metabolism studies with extended-release metformin tablets have not been conducted.

Excretion

Saxagliptin

Saxagliptin is eliminated by both renal and hepatic pathways. Following a single 50 mg dose of ^14C-saxagliptin, 24%, 36%, and 75% of the dose was excreted in the urine as saxagliptin, its active metabolite, and total radioactivity, respectively. The average renal clearance of saxagliptin (~230 mL/min) was greater than the average estimated glomerular filtration rate (~120 mL/min), suggesting some active renal excretion. A total of 22% of the administered radioactivity was recovered in feces representing the fraction of the saxagliptin dose excreted in bile and/or unabsorbed drug from the gastrointestinal tract. Following a single oral dose of saxagliptin 5 mg to healthy subjects, the mean plasma terminal half-life (t1/2) for saxagliptin and its active metabolite was 2.5 and 3.1 hours, respectively.

Metformin HCl

Renal clearance is approximately 3.5 times greater than creatinine clearance, which indicates that tubular secretion is the major route of metformin elimination. Following oral administration, approximately 90% of the absorbed drug is eliminated via the renal route within the first 24 hours, with a plasma elimination half-life of approximately 6.2 hours. In blood, the elimination half-life is approximately 17.6 hours, suggesting that the erythrocyte mass may be a compartment of distribution.

Specific Populations

Geriatric Patients

Saxagliptin

No dosage adjustment is recommended based on age alone. Elderly subjects (65-80 years) had 23% and 59% higher geometric mean Cmax and geometric mean AUC values, respectively, for saxagliptin than young subjects (18-40 years). Differences in active metabolite pharmacokinetics between elderly and young subjects generally reflected the differences observed in saxagliptin pharmacokinetics. The difference between the pharmacokinetics of saxagliptin and the active metabolite in young and elderly subjects is likely due to multiple factors including declining renal function and metabolic capacity with increasing age. Age was not identified as a significant covariate on the apparent clearance of saxagliptin and its active metabolite in the population pharmacokinetic analysis.

Metformin HCl

Limited data from controlled pharmacokinetic studies of metformin in healthy elderly subjects suggest that total plasma clearance of metformin is decreased, the half-life is prolonged, and Cmax is increased, compared to healthy young subjects. From these data, it appears that the change in metformin pharmacokinetics with aging is primarily accounted for by a change in renal function.

Male and Female Patients

Saxagliptin

No dosage adjustment is recommended based on gender. There were no differences observed in saxagliptin pharmacokinetics between males and females. Compared to males, females had approximately 25% higher exposure values for the active metabolite than males, but this difference is unlikely to be of clinical relevance. Gender was not identified as a significant covariate on the apparent clearance of saxagliptin and its active metabolite in the population pharmacokinetic analysis.

Metformin HCl

Metformin pharmacokinetic parameters did not differ significantly between healthy subjects and patients with type 2 diabetes mellitus when analyzed according to gender (males=19, females=16). Similarly, in controlled clinical studies in patients with type 2 diabetes mellitus, the antihyperglycemic effect of metformin was comparable in males and females.

Racial or Ethnic Groups

Saxagliptin

No dosage adjustment is recommended based on race. The population pharmacokinetic analysis compared the pharmacokinetics of saxagliptin and its active metabolite in 309 White subjects with 105 subjects of other races (consisting of six racial groups). No significant difference in the pharmacokinetics of saxagliptin and its active metabolite were detected between these two populations.

Metformin HCl

No studies of metformin pharmacokinetic parameters according to race have been performed. In controlled clinical studies of metformin in patients with type 2 diabetes mellitus, the antihyperglycemic effect was comparable in Whites (n=249), Black or African American (n=51), and Hispanic or Latino ethnicity (n=24).

Patients with Renal Impairment

Saxagliptin

A single-dose, open-label trial was conducted to evaluate the pharmacokinetics of saxagliptin (10 mg dose) in subjects with varying degrees of chronic renal impairment compared to subjects with normal renal function. The 10 mg dosage is not an approved dosage. The degree of renal impairment did not affect Cmax of saxagliptin or its metabolite. In subjects with moderate renal impairment with eGFR 30 to less than 45 mL/min/1.73 m^2, severe renal impairment (eGFR 15 to less than 30 mL/min/1.73 m^2) and ESRD patient on hemodialysis, the AUC values of saxagliptin or its active metabolite were >2 fold higher than AUC values in subjects with normal renal function.

Metformin HCl

In patients with decreased renal function, the plasma and blood half-life of metformin is prolonged and the renal clearance is decreased [see Contraindications (4) and Warnings and Precautions (5.1)].

Patients with Hepatic Impairment

No pharmacokinetic studies of metformin have been conducted in patients with hepatic impairment.

Body Mass Index

Saxagliptin

No dosage adjustment is recommended based on body mass index (BMI) which was not identified as a significant covariate on the apparent clearance of saxagliptin or its active metabolite in the population pharmacokinetic analysis.

Drug Interaction Studies

Specific pharmacokinetic drug interaction studies with KOMBIGLYZE XR have not been performed, although such studies have been conducted with the individual saxagliptin and metformin components.

In Vitro Assessment of Drug Interactions

In in vitro studies, saxagliptin and its active metabolite did not inhibit CYP1A2, 2A6, 2B6, 2C9, 2C19, 2D6, 2E1, or 3A4, or induce CYP1A2, 2B6, 2C9, or 3A4. Therefore, saxagliptin is not expected to alter the metabolic clearance of coadministered drugs that are metabolized by these enzymes. Saxagliptin is a P-glycoprotein (P-gp) substrate, but is not a significant inhibitor or inducer of P-gp.

In Vivo Assessment of Drug Interactions

Table 3: Effect of Coadministered Drug on Systemic Exposures of Saxagliptin and its Active Metabolite, 5-hydroxy Saxagliptin
Coadministered Drug | Dosage of Coadministered Drug [Single dose unless otherwise noted. The 10 mg saxagliptin dose is not an approved dosage.] | Dosage of Saxagliptin | Geometric Mean Ratio (ratio with/without coadministered drug) No Effect = 1.00
 |  |  |  | AUC [AUC = AUC(INF) for drugs given as single dose and AUC = AUC(TAU) for drugs given in multiple doses.] | Cmax
No dosing adjustments required for the following:
Metformin | 1,000 mg | 100 mg | saxagliptin 5-hydroxy saxagliptin | 0.98 0.99 | 0.79 0.88
Glyburide | 5 mg | 10 mg | saxagliptin 5-hydroxy saxagliptin | 0.98 ND | 1.08 ND
Pioglitazone [Results exclude one patient.] | 45 mg QD for 10 days | 10 mg QD for 5 days | saxagliptin 5-hydroxy saxagliptin | 1.11 ND | 1.11 ND
Digoxin | 0.25 mg q6h first day followed by q12h second day followed by QD for 5 days | 10 mg QD for 7 days | saxagliptin 5-hydroxy saxagliptin | 1.05 1.06 | 0.99 1.02
Dapagliflozin | 10 mg single dose | 5 mg single dose | saxagliptin; 5-hydroxy saxagliptin | ↓1%; ↑9% | ↓7%; ↑6%
Simvastatin | 40 mg QD for 8 days | 10 mg QD for 4 days | saxagliptin 5-hydroxy saxagliptin | 1.12 1.02 | 1.21 1.08
Diltiazem | 360 mg LA QD for 9 days | 10 mg | saxagliptin 5-hydroxy saxagliptin | 2.09 0.66 | 1.63 0.57
Rifampin [The plasma dipeptidyl peptidase-4 (DPP4) activity inhibition over a 24-hour dose interval was not affected by rifampin.] | 600 mg QD for 6 days | 5 mg | saxagliptin 5-hydroxy saxagliptin | 0.24 1.03 | 0.47 1.39
Omeprazole | 40 mg QD for 5 days | 10 mg | saxagliptin 5-hydroxy saxagliptin | 1.13 ND | 0.98 ND
Aluminum hydroxide + magnesium hydroxide + simethicone | aluminum hydroxide: 2400 mg magnesium hydroxide: 2400 mg simethicone: 240 mg | 10 mg | saxagliptin 5-hydroxy saxagliptin | 0.97 ND | 0.74 ND
Famotidine | 40 mg | 10 mg | saxagliptin 5-hydroxy saxagliptin | 1.03 ND | 1.14 ND
Limit KOMBIGLYZE XR dose to 2.5 mg/1,000 mg once daily when coadministered with strong CYP3A4/5 inhibitors [see Drug Interactions (7.1) and Dosage and Administration (2.2)]:
Ketoconazole | 200 mg BID for 9 days | 100 mg | saxagliptin 5-hydroxy saxagliptin | 2.45 0.12 | 1.62 0.05
Ketoconazole | 200 mg BID for 7 days | 20 mg | saxagliptin 5-hydroxy saxagliptin | 3.67 ND | 2.44 ND

ND=not determined; QD=once daily; q6h=every 6 hours; q12h=every 12 hours; BID=twice daily; LA=long acting.

Table 4: Effect of Saxagliptin on Systemic Exposures of Coadministered Drugs
Coadministered Drug | Dosage of Coadministered Drug [Single dose unless otherwise noted. The 10 mg saxagliptin dose is not an approved dosage.] | Dosage of Saxagliptin | Geometric Mean Ratio (ratio with/without saxagliptin) No Effect = 1.00
 |  |  |  | AUC [AUC = AUC(INF) for drugs given as single dose and AUC = AUC(TAU) for drugs given in multiple doses.] | Cmax
No dosing adjustments required for the following:
Metformin | 1000 mg | 100 mg | metformin | 1.20 | 1.09
Glyburide | 5 mg | 10 mg | glyburide | 1.06 | 1.16
Pioglitazone [Results include all patients.] | 45 mg QD for 10 days | 10 mg QD for 5 days | pioglitazone hydroxy-pioglitazone | 1.08 ND | 1.14 ND
Digoxin | 0.25 mg q6h first day followed by q12h second day followed by QD for 5 days | 10 mg QD for 7 days | digoxin | 1.06 | 1.09
Simvastatin | 40 mg QD for 8 days | 10 mg QD for 4 days | simvastatin simvastatin acid | 1.04 1.16 | 0.88 1.00
Diltiazem | 360 mg LA QD for 9 days | 10 mg | diltiazem | 1.10 | 1.16
Ketoconazole | 200 mg BID for 9 days | 100 mg | ketoconazole | 0.87 | 0.84
Ethinyl estradiol and norgestimate | ethinyl estradiol 0.035 mg and norgestimate 0.250 mg for 21 days | 5 mg QD for 21 days | ethinyl estradiol norelgestromin norgestrel | 1.07 1.10 1.13 | 0.98 1.09 1.17

ND=not determined; QD=once daily; q6h=every 6 hours; q12h=every 12 hours; BID=twice daily; LA=long acting.

Table 5: Effect of Coadministered Drug on Plasma Metformin Systemic Exposure
Coadministered Drug | Dose of Coadministered Drug [All metformin and coadministered drugs were given as single doses.] | Dose of Metformin | Geometric Mean Ratio (ratio with/without coadministered drug) No Effect = 1.00
 |  |  |  | AUC [AUC = AUC(INF).] | Cmax
No dosing adjustments required for the following:
Glyburide | 5 mg | 850 mg | metformin | 0.91 [Ratio of arithmetic means.] | 0.93
Furosemide | 40 mg | 850 mg | metformin | 1.09 | 1.22
Nifedipine | 10 mg | 850 mg | metformin | 1.16 | 1.21
Propranolol | 40 mg | 850 mg | metformin | 0.90 | 0.94
Ibuprofen | 400 mg | 850 mg | metformin | 1.05 | 1.07
Drugs that are eliminated by renal tubular secretion may increase the accumulation of metformin [see Drug Interactions (7.3)].
Cimetidine | 400 mg | 850 mg | metformin | 1.40 | 1.61

Table 6: Effect of Metformin on Coadministered Drug Systemic Exposure
Coadministered Drug | Dose of Coadministered Drug [All metformin and coadministered drugs were given as single doses.] | Dose of Metformin | Geometric Mean Ratio (ratio with/without metformin) No Effect = 1.00
 |  |  |  | AUC [AUC = AUC(INF) unless otherwise noted.] | Cmax
No dosing adjustments required for the following:
Glyburide | 5 mg | 850 mg | glyburide | 0.78 [Ratio of arithmetic means, p-value of difference <0.05.] | 0.63
Furosemide | 40 mg | 850 mg | furosemide | 0.87 | 0.69
Nifedipine | 10 mg | 850 mg | nifedipine | 1.10 [AUC(0-24 hr) reported.] | 1.08
Propranolol | 40 mg | 850 mg | propranolol | 1.01 | 1.02
Ibuprofen | 400 mg | 850 mg | ibuprofen | 0.97 [Ratio of arithmetic means.] | 1.01
Cimetidine | 400 mg | 850 mg | cimetidine | 0.95 | 1.01

13 NONCLINICAL TOXICOLOGY

13.1 Carcinogenesis, Mutagenesis, Impairment of Fertility

KOMBIGLYZE XR

CARCINOGENESIS AND MUTAGENESIS AND IMPAIRMENT OF FERTILITY

No animal studies have been conducted with the combined products in KOMBIGLYZE XR to evaluate carcinogenesis, mutagenesis, or impairment of fertility. The following data are based on studies with saxagliptin and metformin administered individually.

CARCINOGENESIS AND MUTAGENESIS AND IMPAIRMENT OF FERTILITY

Saxagliptin

Carcinogenesis

Carcinogenicity was evaluated in 2-year studies conducted in CD-1 mice and Sprague-Dawley rats. Saxagliptin did not increase the incidence of tumors in mice dosed orally at 50, 250, and 600 mg/kg up to 870-times (males) and 1165-times (females) the 5 mg/day clinical dose, based on AUC. Saxagliptin did not increase the incidence of tumors in rats dosed orally at 25, 75, 150, and 300 mg/kg up to 355-times (males) and 2217-times (females) the 5 mg/day clinical dose, based on AUC.

Mutagenesis

CARCINOGENESIS AND MUTAGENESIS AND IMPAIRMENT OF FERTILITY

Saxagliptin was not mutagenic or clastogenic in a battery of genotoxicity tests (Ames bacterial mutagenesis, human and rat lymphocyte cytogenetics, rat bone marrow micronucleus and DNA repair assays). The active metabolite of saxagliptin was not mutagenic in an Ames bacterial assay.

Impairment of Fertility

CARCINOGENESIS AND MUTAGENESIS AND IMPAIRMENT OF FERTILITY

Saxagliptin administered to rats had no effect on fertility or the ability to maintain a litter at exposures up to 603-times and 776-times the 5 mg clinical dose in males and females, based on AUC.

Metformin HCI

Carcinogenesis

Long-term carcinogenicity studies have been performed in rats (dosing duration of 104 weeks) and mice (dosing duration of 91 weeks) at doses up to and including 900 mg/kg/day and 1,500 mg/kg/day, respectively. These doses are both approximately 4 times the maximum recommended human daily dose of 2,000 mg based on body surface area comparisons. No evidence of carcinogenicity with metformin was found in either male or female mice. Similarly, there was no tumorigenic potential observed with metformin in male rats. There was, however, an increased incidence of benign stromal uterine polyps in female rats treated with 900 mg/kg/day.

Mutagenesis

There was no evidence of a mutagenic potential of metformin in the following in vitro tests: Ames test (S. typhimurium), gene mutation test (mouse lymphoma cells), or chromosomal aberrations test (human lymphocytes). Results in the in vivo mouse micronucleus test were also negative.

Impairment of Fertility

Fertility of male or female rats was unaffected by metformin when administered at doses as high as 600 mg/kg/day, which is approximately 3 times the maximum recommended human daily dose based on body surface area comparisons.

13.2 Animal Toxicology and/or Pharmacology

ANIMAL PHARMACOLOGY AND OR TOXICOLOGY

Saxagliptin

Saxagliptin produced adverse skin changes in the extremities of cynomolgus monkeys (scabs and/or ulceration of tail, digits, scrotum, and/or nose). Skin lesions were reversible within exposure approximately 20-times the 5 mg clinical dose, but in some cases were irreversible and necrotizing at higher exposures. Adverse skin changes were not observed at exposures similar to (1- to 3-times) the 5 mg clinical dose. Clinical correlates to skin lesions in monkeys have not been observed in human clinical trials of saxagliptin.

14 CLINICAL STUDIES

14.1 Glycemic Efficacy Trials

The effectiveness of KOMBIGLYZE XR has been established in clinical trials of coadministration of oral saxagliptin and metformin HCl immediate-release tablets in adults with type 2 diabetes mellitus inadequately controlled on metformin HCl alone and in treatment-naive patients inadequately controlled on diet and exercise alone. In these two trials, treatment with saxagliptin dosed in the morning plus metformin HCl immediate-release tablets at all doses produced statistically significant improvements in A1C, fasting plasma glucose (FPG), and 2-hour postprandial glucose (PPG) following a standard oral glucose tolerance test (OGTT), compared to control. Reductions in A1C were seen across subgroups including gender, age, race, and baseline BMI.

In these two trials, decrease in body weight in the treatment groups given saxagliptin in combination with metformin HCl immediate-release was similar to that in the groups given metformin HCl immediate-release alone. Saxagliptin plus metformin HCl immediate-release was not associated with significant changes from baseline in fasting serum lipids compared to metformin HCl alone.

The coadministration of saxagliptin and metformin HCl immediate-release tablets has also been evaluated in an active-controlled trial comparing add-on therapy with saxagliptin to glipizide in 858 patients inadequately controlled on metformin HCl alone, in a placebo-controlled trial where a subgroup of 314 patients inadequately controlled on insulin plus metformin HCl received add-on therapy with saxagliptin or placebo, a trial comparing saxagliptin to placebo in 257 patients inadequately controlled on metformin HCl plus a sulfonylurea, and a trial comparing saxagliptin to placebo in 315 patients inadequately controlled on dapagliflozin and metformin HCl.

In a 24-week, double-blind, randomized trial, patients treated with metformin HCl immediate-release 500 mg twice daily for at least 8 weeks were randomized to continued treatment with metformin HCl immediate-release 500 mg twice daily or to metformin HCl extended-release either 1,000 mg once daily or 1,500 mg once daily. The mean change in A1C from baseline to Week 24 was 0.1% (95% confidence interval 0%, 0.3%) for the metformin HCl immediate-release treatment arm, 0.3% (95% confidence interval 0.1%, 0.4%) for the 1,000 mg metformin HCl extended-release treatment arm, and 0.1% (95% confidence interval 0%, 0.3%) for the 1,500 mg metformin HCl extended-release treatment arm. Results of this trial suggest that patients receiving metformin HCl immediate-release treatment may be safely switched to metformin HCl extended-release once daily at the same total daily dose, up to 2,000 mg once daily. Following a switch from metformin HCl immediate-release to metformin HCl extended-release, glycemic control should be closely monitored and dosage adjustments made accordingly.

Saxagliptin Morning and Evening Dosing

A 24-week monotherapy trial was conducted to assess a range of dosing regimens for saxagliptin. Treatment-naive patients with inadequately controlled diabetes (A1C ≥7% to ≤10%) underwent a 2-week, single-blind diet, exercise, and placebo lead-in period. A total of 365 patients were randomized to 2.5 mg every morning, 5 mg every morning, 2.5 mg with possible titration to 5 mg every morning, or 5 mg every evening of saxagliptin, or placebo. Patients who failed to meet specific glycemic goals during the trial were treated with metformin HCI rescue therapy added on to placebo or saxagliptin; the number of patients randomized per treatment group ranged from 71 to 74.

Treatment with either saxagliptin 5 mg every morning or 5 mg every evening provided significant improvements in A1C versus placebo (mean placebo-corrected reductions of −0.4% and −0.3%, respectively).

Coadministration of Saxagliptin with Metformin HCI Immediate-Release in Treatment-Naive Patients

A total of 1306 treatment-naive patients with type 2 diabetes mellitus participated in this 24-week, randomized, double-blind, active-controlled trial to evaluate the efficacy and safety of saxagliptin coadministered with metformin HCl immediate-release in patients with inadequate glycemic control (A1C ≥8% to ≤12%) on diet and exercise alone. Patients were required to be treatment-naive to be enrolled in this trial.

Patients who met eligibility criteria were enrolled in a single-blind, 1-week, dietary and exercise placebo lead-in period. Patients were randomized to one of four treatment arms: saxagliptin 5 mg + metformin HCl immediate-release 500 mg, saxagliptin 10 mg + metformin HCl immediate-release 500 mg, saxagliptin 10 mg + placebo, or metformin HCl immediate-release 500 mg + placebo (the maximum recommended approved saxagliptin dose is 5 mg daily; the 10 mg daily dose of saxagliptin does not provide greater efficacy than the 5 mg daily dose and the 10 mg saxagliptin dosage is not an approved dosage). Saxagliptin was dosed once daily. In the 3 treatment groups using metformin HCl immediate-release, the metformin HCl dose was up-titrated weekly in 500 mg per day increments, as tolerated, to a maximum of 2,000 mg per day based on FPG. Patients who failed to meet specific glycemic goals during this trial were treated with pioglitazone rescue as add-on therapy.

Coadministration of saxagliptin 5 mg plus metformin HCl immediate-release provided significant improvements in A1C, FPG, and PPG compared with placebo plus metformin HCl immediate-release (Table 7).

Table 7: Glycemic Parameters at Week 24 in a Placebo-Controlled Trial of Saxagliptin Coadministration with Metformin Immediate-Release in Treatment-Naive Patients [Intent-to-treat population using last observation on trial or last observation prior to pioglitazone rescue therapy for patients needing rescue.]
Efficacy Parameter | Saxagliptin 5 mg + Metformin HCI N=320 | Placebo + Metformin HCI N=328
Hemoglobin A1C (%) | N=306 | N=313
Baseline (mean) | 9.4 | 9.4
Change from baseline (adjusted mean [Least squares mean adjusted for baseline value.]) | −2.5 | −2.0
Difference from placebo + metformin HCI (adjusted mean) | −0.5 [p-value <0.0001 compared to placebo + metformin HCI.]
95% Confidence Interval | (−0.7, −0.4)
Percent of patients achieving A1C <7% | 60% [p-value <0.05 compared to placebo + metformin HCI.] (185/307) | 41% (129/314)
Fasting Plasma Glucose (mg/dL) | N=315 | N=320
Baseline (mean) | 199 | 199
Change from baseline (adjusted mean) | −60 | −47
Difference from placebo + metformin HCI (adjusted mean) | −13
95% Confidence Interval | (−19, −6)
2-hour Postprandial Glucose (mg/dL) | N=146 | N=141
Baseline (mean) | 340 | 355
Change from baseline (adjusted mean) | −138 | −97
Difference from placebo + metformin HCI (adjusted mean) | −41
95% Confidence Interval | (−57, −25)

Addition of Saxagliptin to Metformin HCI Immediate-Release

A total of 743 patients with type 2 diabetes mellitus participated in this 24-week, randomized, double-blind, placebo-controlled trial to evaluate the efficacy and safety of saxagliptin in combination with metformin HCl immediate-release in patients with inadequate glycemic control (A1C ≥7% and ≤10%) on metformin HCl alone. To qualify for enrollment, patients were required to be on a stable dose of metformin HCl (1,500-2,550 mg daily) for at least 8 weeks.

Patients who met eligibility criteria were enrolled in a single-blind, 2-week, dietary and exercise placebo lead-in period during which patients received metformin HCl immediate-release at their pre-trial dose, up to 2500 mg daily, for the duration of the trial. Following the lead-in period, eligible patients were randomized to 2.5 mg, 5 mg, or 10 mg of saxagliptin or placebo in addition to their current dose of open-label metformin HCl immediate-release (the maximum recommended approved saxagliptin dose is 5 mg daily; the 10 mg daily dose of saxagliptin does not provide greater efficacy than the 5 mg daily dose and the 10 mg dosage is not an approved dosage). Patients who failed to meet specific glycemic goals during the trial were treated with pioglitazone rescue therapy, added on to existing trial medications. Dose titrations of saxagliptin and metformin HCl immediate-release were not permitted.

Saxagliptin 2.5 mg and 5 mg add-on to metformin HCl immediate-release provided significant improvements in A1C, FPG, and PPG compared with placebo add-on to metformin HCl immediate-release (Table 8). Mean changes from baseline for A1C over time and at endpoint are shown in Figure 1. The proportion of patients who discontinued for lack of glycemic control or who were rescued for meeting prespecified glycemic criteria was 15% in the saxagliptin 2.5 mg add-on to metformin HCl immediate-release group, 13% in the saxagliptin 5 mg add-on to metformin HCl immediate-release group, and 27% in the placebo add-on to metformin HCl immediate-release group.

Table 8: Glycemic Parameters at Week 24 in a Placebo-Controlled Trial of Saxagliptin as Add-On Combination Therapy with Metformin HCI Immediate-Release [Intent-to-treat population using last observation on trial or last observation prior to pioglitazone rescue therapy for patients needing rescue.]
Efficacy Parameter | Saxagliptin 2.5 mg + Metformin HCI N=192 | Saxagliptin 5 mg + Metformin HCI N=191 | Placebo + Metformin HCI N=179
Hemoglobin A1C (%) | N=186 | N=186 | N=175
Baseline (mean) | 8.1 | 8.1 | 8.1
Change from baseline (adjusted mean [Least squares mean adjusted for baseline value.]) | −0.6 | −0.7 | +0.1
Difference from placebo (adjusted mean) | −0.7 [p-value <0.0001 compared to placebo + metformin HCI.] | −0.8
95% Confidence Interval | (−0.9, −0.5) | (−1.0, −0.6)
Percent of patients achieving A1C <7% | 37% [p-value <0.05 compared to placebo + metformin HCI.] (69/186) | 44% (81/186) | 17% (29/175)
Fasting Plasma Glucose (mg/dL) | N=188 | N=187 | N=176
Baseline (mean) | 174 | 179 | 175
Change from baseline (adjusted mean) | −14 | −22 | +1
Difference from placebo (adjusted mean) | −16 | −23
95% Confidence Interval | (−23, −9) | (−30, −16)
2-hour Postprandial Glucose (mg/dL) | N=155 | N=155 | N=135
Baseline (mean) | 294 | 296 | 295
Change from baseline (adjusted mean) | −62 | −58 | −18
Difference from placebo (adjusted mean) | −44 | −40
95% Confidence Interval | (−60, −27) | (−56, −24)

Figure 1: Mean Change from Baseline in A1C in a Placebo-Controlled Trial of Saxagliptin as Add-On Combination Therapy with Metformin HCI Immediate-Release*

* Includes patients with a baseline and week 24 value.

Week 24 (LOCF) includes intent-to-treat population using last observation on trial prior to pioglitazone rescue therapy for patients needing rescue. Mean change from baseline is adjusted for baseline value.

Saxagliptin Add-On Combination Therapy with Metformin HCI Immediate-Release versus Glipizide Add-On Combination Therapy with Metformin HCI Immediate-Release

In this 52-week, active-controlled trial, a total of 858 patients with type 2 diabetes mellitus and inadequate glycemic control (A1C >6.5% and ≤10%) on metformin HCl immediate-release alone were randomized to double-blind add-on therapy with saxagliptin or glipizide. Patients were required to be on a stable dose of metformin HCl immediate-release (at least 1,500 mg daily) for at least 8 weeks prior to enrollment.

Patients who met eligibility criteria were enrolled in a single-blind, 2-week, dietary and exercise placebo lead-in period during which patients received metformin HCl immediate-release (1,500-3,000 mg based on their pre-trial dose). Following the lead-in period, eligible patients were randomized to 5 mg of saxagliptin or 5 mg of glipizide in addition to their current dose of open-label metformin HCl immediate-release. Patients in the glipizide plus metformin HCl immediate-release group underwent blinded titration of the glipizide dose during the first 18 weeks of the trial up to a maximum glipizide dose of 20 mg per day. Titration was based on a goal FPG ≤110 mg/dL or the highest tolerable glipizide dose. Fifty percent (50%) of the glipizide-treated patients were titrated to the 20-mg daily dose; 21% of the glipizide-treated patients had a final daily glipizide dose of 5 mg or less. The mean final daily dose of glipizide was 15 mg.

After 52 weeks of treatment, saxagliptin and glipizide resulted in similar mean reductions from baseline in A1C when added to metformin HCl immediate-release therapy (Table 9). This conclusion may be limited to patients with baseline A1C comparable to those in the trial (91% of patients had baseline A1C <9%). From a baseline mean body weight of 89 kg, there was a statistically significant mean reduction of 1.1 kg in patients treated with saxagliptin compared to a mean weight gain of 1.1 kg in patients treated with glipizide (p<0.0001).

From a baseline mean body weight of 89 kg, there was a statistically significant mean reduction of 1.1 kg in patients treated with saxagliptin compared to a mean weight gain of 1.1 kg in patients treated with glipizide (p<0.0001).

Table 9: Glycemic Parameters at Week 52 in an Active-Controlled Trial of Saxagliptin versus Glipizide in Combination with Metformin HCI Immediate-Release [Intent-to-treat population using last observation on trial.]
Efficacy Parameter | Saxagliptin 5 mg + Metformin HCI N=428 | Titrated Glipizide + Metformin HCI N=430
Hemoglobin A1C (%) | N=423 | N=423
Baseline (mean) | 7.7 | 7.6
Change from baseline (adjusted mean [Least squares mean adjusted for baseline value.]) | −0.6 | −0.7
Difference from glipizide + metformin HCI (adjusted mean) | 0.1
95% Confidence Interval | (−0.02, 0.2) [Saxagliptin + metformin HCI is considered non-inferior to glipizide + metformin because the upper limit of this confidence interval is less than the prespecified non-inferiority margin of 0.35%.]
Fasting Plasma Glucose (mg/dL) | N=420 | N=420
Baseline (mean) | 162 | 161
Change from baseline (adjusted mean) | −9 | −16
Difference from glipizide + metformin HCI (adjusted mean) | 6
95% Confidence Interval | (2, 11) [Significance not tested.]

Saxagliptin Add-On Combination Therapy with Insulin (with or without Metformin Immediate-Release)

A total of 455 patients with type 2 diabetes participated in this 24-week, randomized, double-blind, placebo-controlled trial to evaluate the efficacy and safety of saxagliptin in combination with insulin in patients with inadequate glycemic control (A1C ≥7.5% and ≤11%) on insulin alone (N=141) or on insulin in combination with a stable dose of metformin immediate-release (N=314). Patients were required to be on a stable dose of insulin (≥30 units to ≤150 units daily) with ≤20% variation in total daily dose for ≥8 weeks prior to screening. Patients entered the trial on intermediate- or long-acting (basal) insulin or premixed insulin. Patients using short-acting insulins were excluded unless the short-acting insulin was administered as part of a premixed insulin.

Patients who met eligibility criteria were enrolled in a single-blind, four-week, dietary and exercise placebo lead-in period during which patients received insulin (and metformin immediate-release if applicable) at their pretrial dose(s). Following the lead-in period, eligible patients were randomized to add-on therapy with either saxagliptin 5 mg or placebo. Doses of the antidiabetic therapies were to remain stable but patients were rescued and allowed to adjust the insulin regimen if specific glycemic goals were not met or if the investigator learned that the patient had self-increased the insulin dose by >20%. Data after rescue were excluded from the primary efficacy analyses.

Add-on therapy with saxagliptin 5 mg provided significant improvements from baseline to Week 24 in A1C and PPG compared with add-on placebo (Table 10). Similar mean reductions in A1C versus placebo were observed for patients using saxagliptin 5 mg add-on to insulin alone and saxagliptin 5 mg add-on to insulin in combination with metformin immediate-release (−0.4% and −0.4%, respectively). The percentage of patients who discontinued for lack of glycemic control or who were rescued was 23% in the saxagliptin group and 32% in the placebo group.

The mean daily insulin dose at baseline was 53 units in patients treated with saxagliptin 5 mg and 55 units in patients treated with placebo. The mean change from baseline in daily dose of insulin was 2 units for the saxagliptin 5 mg group and 5 units for the placebo group.

Table 10: Glycemic Parameters at Week 24 in a Placebo-Controlled Trial of Saxagliptin as Add-On Combination Therapy with Insulin [Intent-to-treat population using last observation on trial or last observation prior to insulin rescue therapy for patients needing rescue.]
Efficacy Parameter | Saxagliptin 5 mg + Insulin (+/− Metformin HCI) N=304 | Placebo + Insulin (+/− Metformin HCI) N=151
Hemoglobin A1C (%) | N=300 | N=149
Baseline (mean) | 8.7 | 8.7
Change from baseline (adjusted mean [Least squares mean adjusted for baseline value and metformin HCI use at baseline.]) | −0.7 | −0.3
Difference from placebo (adjusted mean) | −0.4 [p-value <0.0001 compared to placebo + insulin.]
95% Confidence Interval | (−0.6, −0.2)
2-hour Postprandial Glucose (mg/dL) | N=262 | N=129
Baseline (mean) | 251 | 255
Change from baseline (adjusted mean) | −27 | −4
Difference from placebo (adjusted mean) | −23 [p-value <0.05 compared to placebo + insulin.]
95% Confidence Interval | (−37, −9)

The change in fasting plasma glucose from baseline to Week 24 was also tested, but was not statistically significant. The percent of patients achieving an A1C <7% was 17% (52/300) with saxagliptin in combination with insulin compared to 7% (10/149) with placebo. Significance was not tested.

Saxagliptin Add-On Combination Therapy with Metformin HCI plus Sulfonylurea

A total of 257 patients with type 2 diabetes mellitus participated in this 24-week, randomized, double-blind, placebo-controlled trial to evaluate the efficacy and safety of saxagliptin in combination with metformin HCl plus a sulfonylurea in patients with inadequate glycemic control (A1C ≥7% and ≤10%). Patients were to be on a stable combined dose of metformin HCl extended-release or immediate-release (at maximum tolerated dose, with minimum dose for enrollment being 1,500 mg) and a sulfonylurea (at maximum tolerated dose, with minimum dose for enrollment being ≥50% of the maximum recommended dose) for 8 weeks prior to enrollment.

Patients who met eligibility criteria were entered in a 2-week enrollment period to allow assessment of inclusion/exclusion criteria. Following the 2-week enrollment period, eligible patients were randomized to either double-blind saxagliptin (5 mg once daily) or double-blind matching placebo for 24 weeks. During the 24-week double-blind treatment period, patients were to receive metformin HCl and a sulfonylurea at the same constant dose ascertained during enrollment. Sulfonylurea dose could be down titrated once in the case of a major hypoglycemic event or recurring minor hypoglycemic events. In the absence of hypoglycemia, titration (up or down) of trial medication during the treatment period was prohibited.

Saxagliptin in combination with metformin HCl plus a sulfonylurea provided significant improvements in A1C and PPG compared with placebo in combination with metformin HCl plus a sulfonylurea (Table 11). The percentage of patients who discontinued for lack of glycemic control was 6% in the saxagliptin group and 5% in the placebo group.

Table 11: Glycemic Parameters at Week 24 in a Placebo-Controlled Trial of Saxagliptin as Add-On Combination Therapy with Metformin HCI plus Sulfonylurea [Intent-to-treat population using last observation prior to discontinuation.]
Efficacy Parameter | Saxagliptin 5 mg + Metformin plus Sulfonylurea N=129 | Placebo + Metformin plus Sulfonylurea N=128
Hemoglobin A1C (%) | N=127 | N=127
Baseline (mean) | 8.4 | 8.2
Change from baseline (adjusted mean [Least squares mean adjusted for baseline value.]) | −0.7 | −0.1
Difference from placebo (adjusted mean) | −0.7 [p-value <0.0001 compared to placebo + metformin HCI plus sulfonylurea.]
95% Confidence Interval | (−0.9, −0.5)
2-hour Postprandial Glucose (mg/dL) | N=115 | N=113
Baseline (mean) | 268 | 262
Change from baseline (adjusted mean) | −12 | 5
Difference from placebo (adjusted mean) | −17 [p-value <0.05 compared to placebo + metformin HCI plus sulfonylurea.]
95% Confidence Interval | (−32, −2)

The change in fasting plasma glucose from baseline to Week 24 was also tested, but was not statistically significant. The percent of patients achieving an A1C <7% was 31% (39/127) with saxagliptin in combination with metformin HCI plus a sulfonylurea compared to 9% (12/127) with placebo. Significance was not tested.

Saxagliptin Add-on Combination Therapy with Metformin plus an SGLT2 Inhibitor

A total of 315 patients with type 2 diabetes mellitus participated in this 24 week randomized, double blind, placebo controlled trial to evaluate the efficacy and safety of saxagliptin added to dapagliflozin (an SGLT2 inhibitor) and metformin HCl in patients with a baseline of HbA1c ≥7% to ≤10.5%. The mean age of these patients was 54.6 years, 1.6% were 75 years or older and 52.7% were female. The population was 87.9% White, 6.3% Black or African American, 4.1% Asian, and 1.6% other races. At baseline the population had diabetes for an average of 7.7 years and a mean HbA1c of 7.9%. The mean eGFR at baseline was 93.4 mL/min/1.73 m^2. Patients were required to be on a stable dose of metformin HCl (≥1,500 mg per day) for at least 8 weeks prior to enrollment. Eligible patients who completed the screening period entered the lead in treatment period, which included 16 weeks of open-label metformin HCl and 10 mg dapagliflozin treatment. Following the lead-in period, eligible patients were randomized to saxagliptin 5 mg (N=153) or placebo (N =162).

The group treated with add-on saxagliptin had statistically significant greater reductions in HbA1c from baseline versus the group treated with placebo (see Table 12).

Table 12: HbA1c Change from Baseline at Week 24 in a Placebo-Controlled Trial of Saxagliptin as Add-On to Dapagliflozin and Metformin HCI [There were 6.5% (n=10) of randomized patients in the saxagliptin arm and 3.1% (n=5) in the placebo arm for whom change from baseline HbA1c data was missing at week 24. Of the patients who discontinued trial medication early, 9.1% (1 of 11) in the saxagliptin arm and 16.7% (1 of 6) in the placebo arm had HbA1c measured at week 24.]
 | Saxagliptin 5 mg; (N=153) [Number of randomized and treated patients.] | Placebo; (N=162)
 | In combination with Dapagliflozin and Metformin HCI
Hemoglobin A1C (%) [Analysis of Covariance including all post-baseline data regardless of rescue or treatment discontinuation. Model estimates calculated using multiple imputation to model washout of the treatment effect using placebo data for all patients having missing Week 24 data.]
Baseline (mean) | 8.0 | 7.9
Change from baseline (adjusted mean [Least squares mean adjusted for baseline value.]); 95% Confidence Interval | −0.5; (−0.6, −0.4) | −0.2; (−0.3, −0.1)
Difference from placebo (adjusted mean); 95% Confidence Interval | −0.4 [p-value <0.0001.]; (−0.5, −0.2)

The known proportion of patients achieving HbA1c <7% at Week 24 was 35.3% in the saxagliptin-treated group compared to 23.1% in the placebo-treated group.

14.2 Cardiovascular Safety Trial

The cardiovascular risk of saxagliptin was evaluated in SAVOR, a multicenter, multinational, randomized, double-blind trial comparing saxagliptin (N=8280) to placebo (N=8212), both administered in combination with standard of care, in adult patients with type 2 diabetes mellitus at high risk for atherosclerotic cardiovascular disease. Of the randomized trial patients, 97.5% completed the trial, and the median duration of follow-up was approximately 2 years. The trial was event-driven, and patients were followed until a sufficient number of events were accrued.

Patients were at least 40 years of age, had A1C ≥6.5%, and multiple risk factors (21% of randomized patients) for cardiovascular disease (age ≥55 years for men and ≥60 years for women plus at least one additional risk factor of dyslipidemia, hypertension, or current cigarette smoking) or established (79% of the randomized patients) cardiovascular disease defined as a history of ischemic heart disease, peripheral vascular disease, or ischemic stroke. The majority of patients were male (67%) and White (75%) with a mean age of 65 years. Approximately 16% of the population had moderate (estimated glomerular filtration rate [eGFR] ≥30 to ≤50 mL/min) to severe (eGFR <30 mL/min) renal impairment, and 13% had a prior history of heart failure. Patients had a median duration of type 2 diabetes mellitus of approximately 10 years, and a mean baseline A1C level of 8.0%. Approximately 5% of patients were treated with diet and exercise only at baseline. Overall, the use of diabetes medications was balanced across treatment groups (metformin 69%, insulin 41%, sulfonylureas 40%, and TZDs 6%). The use of cardiovascular disease medications was also balanced (angiotensin-converting enzyme [ACE] inhibitors or angiotensin receptor blockers [ARBs] 79%, statins 78%, aspirin 75%, beta-blockers 62%, and non-aspirin antiplatelet medications 24%).

The primary analysis in SAVOR was time to first occurrence of a Major Adverse Cardiac Event (MACE). A major adverse cardiac event in SAVOR was defined as a cardiovascular death, or a nonfatal myocardial infarction (MI) or a nonfatal ischemic stroke. The trial was designed as a non-inferiority trial with a pre-specified risk margin of 1.3 for the hazard ratio of MACE, and was also powered for a superiority comparison if non-inferiority was demonstrated.

The results of SAVOR, including the contribution of each component to the primary composite endpoint are shown in Table 13. The incidence rate of MACE was similar in both treatment arms: 3.8 MACE per 100 patient-years on placebo vs. 3.8 MACE per 100 patient-years on saxagliptin. The estimated hazard ratio of MACE associated with saxagliptin relative to placebo was 1.00 with a 95.1% confidence interval of (0.89, 1.12). The upper bound of this confidence interval, 1.12, excluded a risk margin larger than 1.3.

Table 13: Major Adverse Cardiovascular Events (MACE) by Treatment Group in the SAVOR Trial
 | Saxagliptin |  | Placebo |  | Hazard Ratio
 | Number of Patients (%) | Rate per 100 PY | Number of Patients (%) | Rate per 100 PY | (95.1% CI)
Composite of first event of CV death, non-fatal MI or non-fatal ischemic stroke (MACE) | N=8280 | Total PY = 16308.8 | N=8212 | Total PY = 16156.0
Composite of first event of CV death, non-fatal MI or non-fatal ischemic stroke (MACE) | 613 (7.4) | 3.8 | 609 (7.4) | 3.8 | 1.00 (0.89, 1.12)
CV death | 245 (3.0) | 1.5 | 234 (2.8) | 1.4
Non-fatal MI | 233 (2.8) | 1.4 | 260 (3.2) | 1.6
Non-fatal ischemic stroke | 135 (1.6) | 0.8 | 115 (1.4) | 0.7

The Kaplan-Meier-based cumulative event probability is presented in Figure 2 for time to first occurrence of the primary MACE composite endpoint by treatment arm. The curves for both saxagliptin and placebo arms are close together throughout the duration of the trial. The estimated cumulative event probability is approximately linear for both arms, indicating that the incidence of MACE for both arms was constant over the trial duration.

Vital status was obtained for 99% of patients in the trial. There were 798 deaths in the SAVOR trial. Numerically more patients (5.1%) died in the saxagliptin group than in the placebo group (4.6%). The risk of deaths from all cause (Table 14) was not statistically different between the treatment groups (HR: 1.11; 95.1% CI: 0.96, 1.27).

Table 14: All-Cause Mortality by Treatment Group in the SAVOR Trial
 | Saxagliptin |  | Placebo |  | Hazard Ratio
 | Number of Patients (%) | Rate per 100 PY | Number of Patients (%) | Rate per 100 PY | (95.1% CI)
 | N=8280 | PY=16645.3 | N=8212 | PY=16531.5
All-cause mortality | 420 (5.1) | 2.5 | 378 (4.6) | 2.3 | 1.11 (0.96, 1.27)
CV death | 269 (3.2) | 1.6 | 260 (3.2) | 1.6
Non-CV death | 151 (1.8) | 0.9 | 118 (1.4) | 0.7

16 HOW SUPPLIED/STORAGE AND HANDLING

How Supplied

KOMBIGLYZE® XR (saxagliptin and metformin HCl extended-release) tablets have markings on both sides and are available in the strengths and packages listed in Table 15.

Table 15: KOMBIGLYZE XR Tablet Presentations
Tablet Strength (saxagliptin and metformin HCl extended-release) | Film-Coated Tablet Color/Shape | Tablet Markings | Package Size | NDC Code
5 mg/500 mg | light brown to brown, biconvex, capsule-shaped | “5/500” on one side and “4221” on the reverse, in blue ink | Bottles of 30 | 0310-6135-30
5 mg/1,000 mg | pink, biconvex, capsule-shaped | “5/1000” on one side and “4223” on the reverse, in blue ink | Bottles of 30 | 0310-6145-30
2.5 mg/1,000 mg | pale yellow to light yellow, biconvex, capsule-shaped | “2.5/1000” on one side and “4222” on the reverse, in blue ink | Bottles of 60 | 0310-6125-60

Storage and Handling

Store at 20°C to 25°C (68°F to 77°F); excursions permitted between 15°C and 30°C (59°F and 86°F) [see USP Controlled Room Temperature].

17 PATIENT COUNSELING INFORMATION

Advise the patient to read the FDA-approved patient labeling (Medication Guide).

Lactic Acidosis

The risks of lactic acidosis due to the metformin component, its symptoms and conditions that predispose to its development, as noted in Warnings and Precautions (5.1), should be explained to patients. Patients should be advised to discontinue KOMBIGLYZE XR immediately and to promptly notify their health care provider if unexplained hyperventilation, myalgia, malaise, unusual somnolence, dizziness, slow or irregular heartbeat, sensation of feeling cold (especially in the extremities), or other nonspecific symptoms occur. Gastrointestinal symptoms are common during initiation of metformin treatment and may occur during initiation of KOMBIGLYZE XR therapy; however, patients should consult their physician if they develop unexplained symptoms. Although gastrointestinal symptoms that occur after stabilization are unlikely to be drug related, such an occurrence of symptoms should be evaluated to determine if it may be due to lactic acidosis or other serious disease.

Patients should be counseled against excessive alcohol intake while receiving KOMBIGLYZE XR.

Patients should be informed about the importance of regular testing of renal function and hematological parameters when receiving treatment with KOMBIGLYZE XR.

Instruct patients to inform their doctor that they are taking KOMBIGLYZE XR prior to any surgical or radiological procedure, as temporary discontinuation of KOMBIGLYZE XR may be required until renal function has been confirmed to be normal [see Warnings and Precautions (5.1)].

Pancreatitis

Inform patients that acute pancreatitis has been reported during post-marketing use of saxagliptin. Educate patients that persistent severe abdominal pain, sometimes radiating to the back, which may or may not be accompanied by vomiting, is the hallmark symptom of acute pancreatitis. Instruct patients to promptly discontinue KOMBIGLYZE XR and contact their health care provider if persistent severe abdominal pain occurs [see Warnings and Precautions (5.2)].

Heart Failure

Inform patients of the signs and symptoms of heart failure. Before initiating KOMBIGLYZE XR, ask patients if they have a history of heart failure or other risk factors for heart failure including moderate to severe renal impairment. Instruct patients to contact their health care provider as soon as possible if they experience symptoms of heart failure, including increasing shortness of breath, rapid increase in weight or swelling of the feet [see Warnings and Precautions (5.3)].

Hypoglycemia with Concomitant Use with Insulin or Insulin Secretagogues

Inform patients that hypoglycemia can occur, particularly when insulin or an insulin secretagogue is used in combination with KOMBIGLYZE XR. Educate patients about the risks, symptoms and appropriate management of hypoglycemia [see Warnings and Precautions (5.5)].

Hypersensitivity Reactions

Patients should be informed that serious allergic (hypersensitivity) reactions, such as angioedema, anaphylaxis, and exfoliative skin conditions, have been reported during post-marketing use of saxagliptin. If symptoms of these allergic reactions (such as rash, skin flaking or peeling, urticaria, swelling of the skin, or swelling of the face, lips, tongue, and throat that may cause difficulty in breathing or swallowing) occur, patients must stop taking KOMBIGLYZE XR and seek medical advice promptly [see Warnings and Precautions (5.6)].

Severe and Disabling Arthralgia

Inform patients that severe and disabling joint pain may occur with this class of drugs. The time to onset of symptoms can range from one day to years. Instruct patients to seek medical advice if severe joint pain occurs [see Warnings and Precautions (5.7)].

Bullous Pemphigoid

Inform patients that bullous pemphigoid may occur with this class of drugs. Instruct patients to seek medical advice if blisters or erosions occur [see Warnings and Precautions (5.8)].

Administration Instructions

Patients should be informed that KOMBIGLYZE XR must be swallowed whole and not crushed or chewed, and that the inactive ingredients may occasionally be eliminated in the feces as a soft mass that may resemble the original tablet.

Missed Dose

If a dose is missed, advise patients to take KOMBIGLYZE XR as soon as they remember unless it is time for their next dose Instruct patients not to take two doses of KOMBLIGLYZE XR at the same time.

ONGLYZA® is a registered trademark of the AstraZeneca group of companies.
KOMBIGLYZE® XR is a registered trademark of the AstraZeneca group of companies.

Distributed by:
AstraZeneca Pharmaceuticals LP
Wilmington, DE 19850

MEDICATION GUIDE

KOMBIGLYZE® XR (kom-be-glyze X-R)

(saxagliptin and metformin hydrochloride extended-release)

tablets, for oral use

What is the most important information I should know about KOMBIGLYZE XR?

Serious side effects can happen in people taking KOMBIGLYZE XR, including:

1. Lactic acidosis. Metformin, one of the medicines in KOMBIGLYZE XR, can cause a rare but serious condition called lactic acidosis (a build-up of an acid in the blood) that can cause death. Lactic acidosis is a medical emergency and must be treated in the hospital.

Stop taking KOMBIGLYZE XR and call your healthcare provider right away or go to the nearest hospital emergency room if you have any of the following symptoms of lactic acidosis:

- feel very weak or tired
- you have unusual (not normal) muscle pain
- you have trouble breathing
- you have stomach pains, nausea, vomiting or diarrhea
- have unusual sleepiness or sleep longer than usual
- feel cold, especially in your arms and legs
- feel dizzy or lightheaded
- have a slow or irregular heartbeat

Most people who have had lactic acidosis with metformin have other things that, combined with the metformin, led to the lactic acidosis. Tell your doctor if you have any of the following, because you have a higher chance for getting lactic acidosis with KOMBIGLYZE XR if you:

- have severe kidney problems or your kidneys are affected by certain x-ray tests that use injectable dye
- have liver problems
- drink alcohol very often, or drink a lot of alcohol in short-term "binge" drinking
- get dehydrated (lose a large amount of body fluids). This can happen if you are sick with a fever, vomiting, or diarrhea. Dehydration can also happen when you sweat a lot with activity or exercise and do not drink enough fluids
- are 65 years of age or older
- have surgery
- have a heart attack, severe infection, or stroke

The best way to keep from having a problem with lactic acidosis from metformin is to tell your doctor if you have any of the problems in the list above. Your doctor may decide to stop your KOMBIGLYZE XR for a while if you have any of these things.

KOMBIGLYZE XR can have other serious side effects. See “What are the possible side effects of KOMBIGLYZE XR?”.

2. Inflammation of the pancreas (pancreatitis) which may be severe and lead to death.

Certain medical problems make you more likely to get pancreatitis.

Before you start taking KOMBIGLYZE XR:

Tell your healthcare provider if you have ever had:

• inflammation of your pancreas (pancreatitis) • stones in your gallbladder (gallstones)

• a history of alcoholism • high blood triglyceride levels

Stop taking KOMBIGLYZE XR and contact your healthcare provider right away if you have pain in your stomach area (abdomen) that is severe and will not go away. The pain may be felt going from your abdomen through to your back. The pain may happen with or without vomiting. These may be symptoms of pancreatitis.

3. Heart failure. Heart failure means your heart does not pump blood well enough.

Before you start taking KOMBIGLYZE XR:

Tell your healthcare provider if you

- have ever had heart failure or have problems with your kidneys.

Contact your healthcare provider right away if you have any of the following symptoms:

- increasing shortness of breath or trouble breathing, especially when you lie down
- an unusually fast increase in weight
- unusual tiredness
- swelling or fluid retention, especially in the feet, ankles or legs

These may be symptoms of heart failure.

What is KOMBIGLYZE XR?

- KOMBIGLYZE XR is a prescription medicine that contains saxagliptin and metformin hydrochloride (HCl). KOMBIGLYZE XR is used along with diet and exercise to help control high blood sugar in adults with type 2 diabetes.
- KOMBIGLYZE XR is not recommended for people with type 1 diabetes.
- KOMBIGLYZE XR is not recommended for people with diabetic ketoacidosis (increased ketones in your blood or urine).

It is not known if KOMBIGLYZE XR is safe and effective in children.

Who should not take KOMBIGLYZE XR?

Do not take KOMBIGLYZE XR if you:

- have kidney problems.
- have a condition called metabolic acidosis or diabetic ketoacidosis (increased ketones in your blood or urine).
- are allergic to metformin HCl, saxagliptin, or any of the ingredients in KOMBIGLYZE XR. See the end of this Medication Guide for a complete list of ingredients in KOMBIGLYZE XR.

Symptoms of a serious allergic reaction to KOMBIGLYZE XR may include:

  - swelling of your face, lips, throat, and other areas on your skin
  - difficulty with swallowing or
  - breathing
  - raised, red areas on your skin (hives)
  - skin rash, itching, flaking, or peeling

If you have these symptoms, stop taking KOMBIGLYZE XR and contact your healthcare provider right away.

Before taking KOMBIGLYZE XR, tell your healthcare provider about all of your medical conditions, including if you:

- have type 1 diabetes or have had diabetic ketoacidosis.
- have kidney problems.
- have liver problems.
- have heart problems, including congestive heart failure.
- are older than 80 years. If you are over 80 years old you should not take KOMBIGLYZE XR unless your kidneys have been checked and they are normal.
- drink alcohol very often, or drink a lot of alcohol in short-term "binge" drinking.
- are going to get an injection of dye or contrast agents for an x-ray procedure or if you are going to have surgery and will not be able to eat or drink much. In these situations, KOMBIGLYZE XR may need to be stopped for a short time. Talk to your healthcare provider about when you should stop KOMBIGLYZE XR and when you should start KOMBIGLYZE XR again. See “What is the most important information I should know about KOMBIGLYZE XR?”
- have low levels of vitamin B12 in your blood.
- are pregnant or plan to become pregnant. It is not known if KOMBIGLYZE XR will harm your unborn baby. If you are pregnant, talk with your healthcare provider about the best way to control your blood sugar while you are pregnant.
- are breastfeeding or plan to breastfeed. It is not known if KOMBIGLYZE XR passes into your breast milk. Talk with your healthcare provider about the best way to feed your baby while you take KOMBIGLYZE XR.

Tell your healthcare provider about all the medicines you take, including prescription and over-the-counter medicines, vitamins, and herbal supplements.

Know the medicines you take. Keep a list of them to show your healthcare provider and pharmacist when you get a new medicine. KOMBIGLYZE XR may affect the way other medicines work, and other medicines may affect how KOMBIGLYZE XR works.

Tell your healthcare provider if you will be starting or stopping certain other types of medicines, such as antibiotics, or medicines that treat fungus or HIV/AIDS, because your dose of KOMBIGLYZE XR might need to be changed.

How should I take KOMBIGLYZE XR?

- Take KOMBIGLYZE XR exactly as your healthcare provider tells you.
- KOMBIGLYZE XR should be taken with meals to help lessen an upset stomach side effect.
- Swallow KOMBIGLYZE XR whole. Do not crush, cut, or chew KOMBIGLYZE XR.
- You may sometimes pass a soft mass in your stools (bowel movement) that looks like KOMBIGLYZE XR tablets.
- Your healthcare provider should do blood tests to check how well your kidneys are working before and during your treatment with KOMBIGLYZE XR.
- Check your blood sugar as your healthcare provider tells you to.
- Stay on your prescribed diet and exercise program while taking KOMBIGLYZE XR.
- If you miss a dose of KOMBIGLYZE XR, take it as soon as you remember. If it is almost time for your next dose, skip the missed dose. Just take your next dose as prescribed. Do not take 2 doses of KOMBIGLYZE XR at the same time.
- If you take too much KOMBIGLYZE XR, contact the Poison Help line at 1-800-222-1222 or get medical help right away. Advice is also available online at poisonhelp.org.

What are the possible side effects of KOMBIGLYZE XR?

KOMBIGLYZE XR can cause serious side effects, including:

- See "What is the most important information I should know about KOMBIGLYZE XR?"
- Low vitamin B12 (vitamin B12 deficiency). Using metformin for long periods of time may cause a decrease in the amount of vitamin B12 in your blood, especially if you have had low vitamin B12 levels before. Your healthcare provider may do blood tests to check your vitamin B12 levels.
- Low blood sugar (hypoglycemia). If you take KOMBIGLYZE XR with another medicine that can cause low blood sugar, such as a sulfonylurea or insulin, your risk of getting low blood sugar is higher. The dose of your sulfonylurea medicine or insulin may need to be lowered while you take KOMBIGLYZE XR Symptoms of low blood sugar include:
  o shaking o sweating o rapid heartbeat o change in vision
  o hunger o headache o change in mood o
- Allergic (hypersensitivity) reactions, such as:
- swelling of your face, lips, throat, and other areas on your skin
- difficulty with swallowing or breathing
- raised, red areas on your skin (hives)
- skin rash, itching, flaking, or peeling
  If you have these symptoms, stop taking KOMBIGLYZE XR and contact your healthcare provider right away.
- Joint pain. Some people who take medicines called DPP-4 inhibitors, one of the medicines in KOMBIGLYZE XR, may develop joint pain that can be severe. Call your healthcare provider if you have severe joint pain.
- Skin reaction. Some people who take medicines called DPP-4 inhibitors, one of the medicines in KOMBIGLYZE XR, may develop a skin reaction called bullous pemphigoid that can require treatment in a hospital. Tell your healthcare provider right away if you develop blisters or the breakdown of the outer layer of your skin (erosion). Your healthcare provider may tell you to stop taking KOMBIGLYZE XR.

Common side effects of KOMBIGLYZE XR include:

• upper respiratory tract infection• stuffy or runny nose and sore throat • urinary tract infection

• headache • diarrhea • nausea and vomiting

Swelling or fluid retention in your hands, feet, or ankles (peripheral edema) may become worse in people who also take a thiazolidinedione to treat diabetes. If you do not know whether you are already on this type of medication, ask your healthcare provider.

These are not all of the possible side effects of KOMBIGLYZE XR.

Call your doctor for medical advice about side effects. You may report side effects to FDA at 1-800-FDA-1088.

How should I store KOMBIGLYZE XR?

Store KOMBIGLYZE XR between 68°F to 77°F (20°C to 25°C).

Keep KOMBIGLYZE XR and all medicines out of the reach of children.

General information about the use of KOMBIGLYZE XR

Medicines are sometimes prescribed for purposes other than those listed in a Medication Guide. Do not use KOMBIGLYZE XR for a condition for which it was not prescribed. Do not give KOMBIGLYZE XR to other people, even if they have the same symptoms you have. It may harm them.

You can ask your pharmacist or healthcare provider for information about KOMBIGLYZE XR that is written for health professionals.

What are the ingredients of KOMBIGLYZE XR?

Active ingredients: saxagliptin and metformin HCl.

Inactive ingredients in each tablet: carboxymethylcellulose sodium, hypromellose 2208, and magnesium stearate.

The 5 mg/500 mg tablet also contains: microcrystalline cellulose and hypromellose 2910.

Tablet film coat contains: polyvinyl alcohol, polyethylene glycol 3350, titanium dioxide, talc, and iron oxides.

KOMBIGLYZE XR is a registered trademark of the AstraZeneca group of companies. Distributed by: AstraZeneca Pharmaceuticals LP, Wilmington, DE 19850. For more information, go to www.kombiglyzexr.com or call 1-800-236-9933

This Medication Guide has been approved by the U.S. Food and Drug Administration. Revised:10/2024

PACKAGE/LABEL PRINCIPAL DISPLAY PANEL – 2.5 mg/1000 mg

60 Tablets NDC 0310-6125-60
kombiglyze® XR
(saxagliptin and metformin HCl

extended-release) tablets
2.5 mg/1000 mg
DISPENSE WITH MEDICATION GUIDE
Rx only
Do not crush, cut, or chew tablets.

Tablets must be swallowed whole.
AstraZeneca

PACKAGE/LABEL PRINCIPAL DISPLAY PANEL – 5 mg/500 mg

30 Tablets NDC 0310-6135-30
kombiglyze® XR
(saxagliptin and metformin HCl extended-release) tablets
5 mg/500 mg
DISPENSE WITH MEDICATION GUIDE
Rx only
Do not crush, cut, or chew tablets.

Tablets must be swallowed whole.
AstraZeneca

PACKAGE/LABEL PRINCIPAL DISPLAY PANEL – 5 mg/1000 mg

30 Tablets
NDC 0310-6145-30
Kombiglyze® XR
(saxagliptin and metformin HCl

extended-release) tablets
5 mg/1000 mg
DISPENSE WITH MEDICATION GUIDE
Rx only
Do not crush, cut, or chew tablets.

Tablets must be swallowed whole.
AstraZeneca